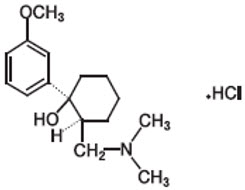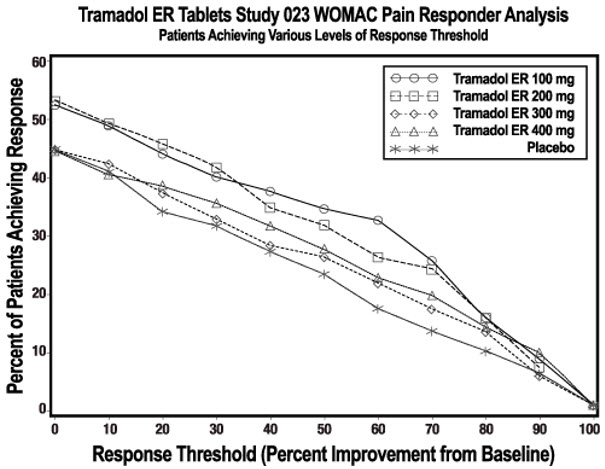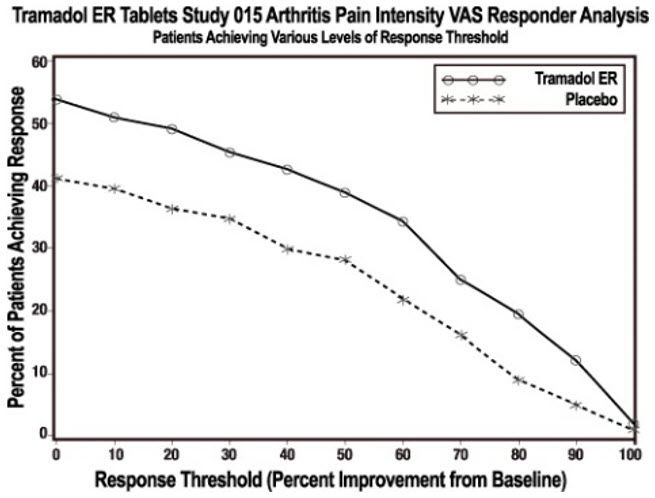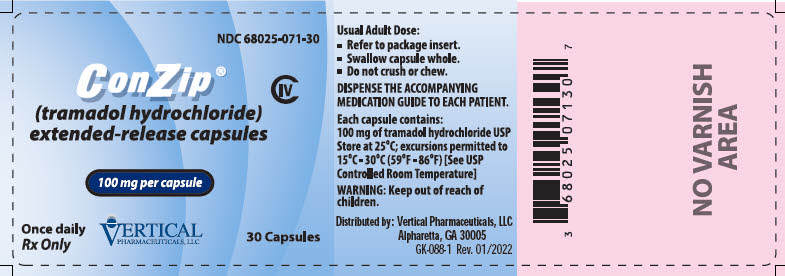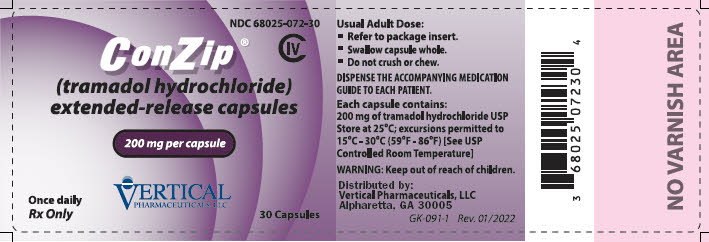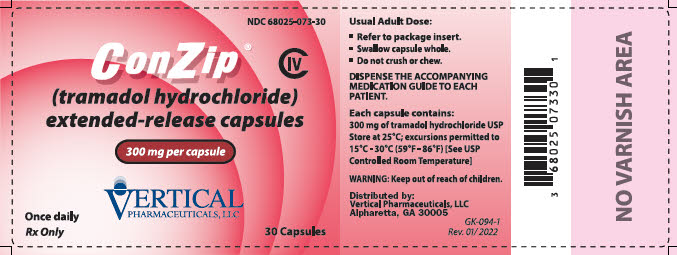 DRUG LABEL: ConZip
NDC: 68025-071 | Form: CAPSULE, EXTENDED RELEASE
Manufacturer: Vertical Pharmaceuticals, LLC
Category: prescription | Type: HUMAN PRESCRIPTION DRUG LABEL
Date: 20251229
DEA Schedule: CIV

ACTIVE INGREDIENTS: TRAMADOL HYDROCHLORIDE 100 mg/1 1
INACTIVE INGREDIENTS: SODIUM STARCH GLYCOLATE TYPE A; GELATIN, UNSPECIFIED; TITANIUM DIOXIDE; SHELLAC; FD&C BLUE NO. 2; LACTOSE MONOHYDRATE; MICROCRYSTALLINE CELLULOSE; SUCROSE STEARATE; POVIDONE K30; STARCH, CORN; MAGNESIUM STEARATE; HYPROMELLOSE 2910 (6 MPA.S); TALC; POLYSORBATE 80; ETHYL ACRYLATE AND METHYL METHACRYLATE COPOLYMER (2:1; 750000 MW)

HIGHLIGHTS OF PRESCRIBING INFORMATION

These highlights do not include all the information needed to use CONZIP® safely and effectively. See full prescribing information for CONZIP®.
CONZIP® (tramadol hydrochloride) extended-release capsules for oral use, CIV
Initial U.S. Approval: 1995

WARNING: SERIOUS AND LIFE-THREATENING RISKS FROM USE OF CONZIP

See full prescribing information for complete boxed warning.

- CONZIP exposes users to risks of addiction, abuse, and misuse, which can lead to overdose and death. Assess patient's risk before prescribing and reassess regularly for these behaviors and conditions. (5.1)
- Serious, life-threatening, or fatal respiratory depression may occur, especially during initiation or following a dosage increase. To reduce the risk of respiratory depression, proper dosing and titration are essential. Instruct patients to swallow CONZIP capsules intact, and not to split, chew, crush, or dissolve content of the capsules to avoid exposure to a potentially fatal dose of tramadol. (2.1, 5.2)
- Accidental ingestion of CONZIP, especially by children, can result in a fatal overdose of tramadol. (5.2)
- Concomitant use of opioids with benzodiazepines or other central nervous system (CNS) depressants, including alcohol, may result in profound sedation, respiratory depression, coma, and death. Reserve concomitant prescribing for use in patients for whom alternative treatment options are inadequate. (5.3, 7)
- Advise pregnant women using opioids for an extended period of time of the risk of Neonatal Opioid Withdrawal Syndrome, which may be life-threatening if not recognized and treated. Ensure that management by neonatology experts will be available at delivery. (5.4)
- Healthcare providers are strongly encouraged to complete a REMS-compliant education program and to counsel patients and caregivers on serious risks, safe use, and the importance of reading the Medication Guide with each prescription. (5.5)
- CONZIP is contraindicated in children younger than 12 years of age and in children younger than 18 years of age following tonsillectomy and/or adenoidectomy. (4) Avoid the use of CONZIP in adolescents 12 to 18 years of age who have other risk factors that may increase their sensitivity to the respiratory depressant effects of tramadol. (5.6)
- The effects of concomitant use or discontinuation of cytochrome P450 3A4 inducers, 3A4 inhibitors, or 2D6 inhibitors with tramadol are complex. Use of cytochrome P450 3A4 inducers, 3A4 inhibitors, or 2D6 inhibitors with CONZIP requires careful consideration of the effects on the parent drug, tramadol, and the active metabolite, M1. (5.7, 7)

RECENT MAJOR CHANGES

Boxed Warning | 12/2025
Indications and Usage (1) | 12/2025
Dosage and Administration (2.1, 2.2, 2.3, 2.5) | 12/2025
Warnings and Precautions (5.1, 5.2, 5.3, 5.10, 5.16, 5.18) | 12/2025

1 INDICATIONS AND USAGE

CONZIP is an opioid agonist indicated for the management of severe and persistent pain that requires an opioid analgesic and that cannot be adequately treated with alternative options, including immediate-release opioids. (1)

Limitations of Use

- Because of the risks of addiction, abuse, misuse, overdose, and death, which can occur at any dosage or duration and persist over the course of therapy, reserve opioid analgesics, including CONZIP, for use in patients for whom alternative treatment options are ineffective, not tolerated, or would be otherwise inadequate to provide sufficient management of pain. (1, 5.1)
- CONZIP is not indicated as an as-needed (prn) analgesic. (1)

2 DOSAGE AND ADMINISTRATION

- CONZIP should be prescribed only by healthcare professionals who are knowledgeable about the use of extended-release/long-acting opioids and how to mitigate the associated risks. (2.1)
- Use the lowest effective dosage for the shortest duration of time consistent with individual patient treatment goals. Reserve titration to higher doses of CONZIP for patients in whom lower doses are insufficiently effective and in whom the expected benefits of using a higher dose opioid clearly outweigh the substantial risks. (2, 5)
- Initiate the dosing regimen for each patient individually, taking into account the patient's underlying cause and severity of pain, prior analgesic treatment and response, and risk factors for addiction, abuse, and misuse. (2.1, 5.1)
- Respiratory depression can occur at any time during opioid therapy, especially when initiating and following dosage increases with CONZIP. Consider this risk when selecting an initial dose and when making dose adjustments. (2.1, 5.2)
- CONZIP is administered orally once daily. (2.1)
- Discuss opioid overdose reversal agents and options for acquiring them with the patient and/or caregiver, both when initiating and renewing treatment with CONZIP, especially if the patient has additional risk factors for overdose, or close contacts at risk for exposure and overdose. (2.2, 5.1, 5.2, 5.3)
- For patients currently on tramadol IR: Calculate total 24-hr IR dose, and initiate CONZIP at a dose rounded down to next lower 100 mg increment; then adjust dose according to need and tolerance. See full prescribing information for instructions on conversion, titration, and maintenance of therapy. (2.3, 2.4)
- For patients converting from other opioid analgesics: Discontinue all other opioid analgesics other than as needed for breakthrough pain and initiate CONZIP at a dose of 100 mg once daily, then titrate up by 100 mg increments every 5 days according to need and tolerance. (2.3, 2.4)
- Do not exceed a daily dose of 300 mg tramadol. Do not use with other tramadol products. (2.4)
- Periodically reassess patients receiving CONZIP to evaluate the continued need for opioid analgesics to maintain pain control, for the signs or symptoms of adverse reactions, and for the development of addiction, abuse, or misuse. (2.4)
- Do not rapidly reduce or abruptly discontinue CONZIP in a physically-dependent patient because rapid reduction or abrupt discontinuation of opioid analgesics has resulted in serious withdrawal symptoms, uncontrolled pain, and suicide. (2.5, 5.18)

3 DOSAGE FORMS AND STRENGTHS

Extended-release capsules: 100 mg, 200 mg, and 300 mg (3)

4 CONTRAINDICATIONS

- Children younger than 12 years of age. (4)
- Postoperative management in children younger than 18 years of age following tonsillectomy and/or adenoidectomy. (4)
- Significant respiratory depression. (4)
- Acute or severe bronchial asthma in an unmonitored setting or in absence of resuscitative equipment. (4)
- Known or suspected gastrointestinal obstruction, including paralytic ileus. (4)
- Hypersensitivity to tramadol. (4)
- Concurrent use of monoamine oxidase inhibitors (MAOIs) or use within the last 14 days. (4)

5 WARNINGS AND PRECAUTIONS

- Opioid-Induced Hyperalgesia and Allodynia: Opioid-Induced Hyperalgesia (OIH) occurs when an opioid analgesic paradoxically causes an increase in pain, or an increase in sensitivity to pain. If OIH is suspected, carefully consider appropriately decreasing the dose of the current opioid analgesic or opioid rotation. (5.8)
- Serotonin Syndrome Risk: Potentially life-threatening condition could result from use of CONZIP, particularly during concomitant use of serotonergic drugs. (5.9)
- Increased Risk of Seizures: Present within recommended dosage range. Risk is increased with higher than recommended doses and concomitant use of SSRIs, SNRIs, anorectics, tricyclic antidepressants and other tricyclic compounds, other opioids, MAOIs, neuroleptics, other drugs that reduce seizure threshold, in patients with epilepsy or at risk for seizures. (5.10, 7)
- Suicide Risk: Do not use CONZIP in suicidal or addiction-prone patients. Use with caution in those taking tranquilizers, antidepressants or abuse alcohol. (5.11)
- Life-Threatening Respiratory Depression in Patients with Chronic Pulmonary Disease or in Elderly, Cachectic, or Debilitated Patients: Regularly evaluate, particularly during initiation and titration. (5.12)
- Adrenal Insufficiency: If diagnosed, treat with physiologic replacement of corticosteroids, and wean patient off of the opioid. (5.13)
- Severe Hypotension: Regularly evaluate during dosage initiation and titration. Avoid use of CONZIP in patients with circulatory shock. (5.14)
- Risks of Use in Patients with Increased Intracranial Pressure, Brain Tumors, Head Injury, or Impaired Consciousness: Monitor for sedation and respiratory depression. Avoid use of CONZIP in patients with impaired consciousness or coma. (5.15)

6 ADVERSE REACTIONS

Most common adverse reactions (incidence ≥10% and twice placebo) are nausea, constipation, dry mouth, somnolence, dizziness, and vomiting. (6)

To report SUSPECTED ADVERSE REACTIONS, contact Vertical Pharmaceuticals, LLC at 1-800-541-4802 or FDA at 1-800-FDA-1088 or www.fda.gov/medwatch.

7 DRUG INTERACTIONS

Mixed Agonist/Antagonist and Partial Agonist Opioid Analgesics: Avoid use with CONZIP because they may reduce analgesic effect of CONZIP or precipitate withdrawal symptoms. (5.18, 7)

8 USE IN SPECIFIC POPULATIONS

- Pregnancy: May cause fetal harm. (8.1)
- Lactation: Breastfeeding not recommended. (8.2)
- Severe Hepatic or Renal Impairment: Use not recommended. (8.6, 8.7)

FULL PRESCRIBING INFORMATION

WARNING: SERIOUS AND LIFE-THREATENING RISKS FROM USE OF CONZIP

Addiction, Abuse, and Misuse

Because the use of CONZIP exposes patients and other users to the risks of opioid addiction, abuse, and misuse, which can lead to overdose and death, assess each patient's risk prior to prescribing and reassess all patients regularly for the development of these behaviors and conditions [see Warnings and Precautions (5.1)].

Life-Threatening Respiratory Depression

Serious, life-threatening, or fatal respiratory depression may occur with use of CONZIP, especially during initiation or following a dosage increase. To reduce the risk of respiratory depression, proper dosing and titration of CONZIP are essential. Instruct patients to swallow CONZIP capsules intact, and not to split, break, chew, crush, or dissolve the contents of the capsules to avoid exposure to a potentially fatal dose of tramadol. [see Dosage and Administration (2.1), Warnings and Precautions (5.2)].

Accidental Ingestion

Accidental ingestion of even one dose of CONZIP, especially by children, can result in a fatal overdose of tramadol [see Warnings and Precautions (5.2)].

Risks From Concomitant Use With Benzodiazepines Or Other CNS Depressants

Concomitant use of opioids with benzodiazepines or other central nervous system (CNS) depressants, including alcohol, may result in profound sedation, respiratory depression, coma, and death. Reserve concomitant prescribing of CONZIP and benzodiazepines or other CNS depressants for use in patients for whom alternative treatment options are inadequate [see Warnings and Precautions (5.3), Drug Interactions (7)].

Neonatal Opioid Withdrawal Syndrome (NOWS)

Advise pregnant women using opioids for an extended period of time of the risk of Neonatal Opioid Withdrawal Syndrome, which may be life-threatening if not recognized and treated. Ensure that management by neonatology experts will be available at delivery [see Warnings and Precautions (5.4)].

Opioid Analgesic Risk Evaluation and Mitigation Strategy (REMS)

Healthcare providers are strongly encouraged to complete a REMS-compliant education program and to counsel patients and caregivers on serious risks, safe use, and the importance of reading the Medication Guide with each prescription [see Warnings and Precautions (5.5)].

Ultra-Rapid Metabolism Of Tramadol And Other Risk Factors for Life-Threatening Respiratory Depression in Children

Life-threatening respiratory depression and death have occurred in children who received tramadol. Some of the reported cases occurred following tonsillectomy and/or adenoidectomy, and in at least one case, the child had evidence of being an ultra-rapid metabolizer of tramadol due to a CYP2D6 polymorphism [see Warnings and Precautions (5.6)]. CONZIP is contraindicated in children younger than 12 years of age and in children younger than 18 years of age following tonsillectomy and/or adenoidectomy [see Contraindications (4)]. Avoid the use of CONZIP in adolescents 12 to 18 years of age who have other risk factors that may increase their sensitivity to the respiratory depressant effects of tramadol [see Warnings and Precautions (5.6)].

Interactions with Drugs Affecting Cytochrome P450 Isoenzymes

The effects of concomitant use or discontinuation of cytochrome P450 3A4 inducers, 3A4 inhibitors, or 2D6 inhibitors with tramadol are complex. Use of cytochrome P450 3A4 inducers, 3A4 inhibitors, or 2D6 inhibitors with CONZIP requires careful consideration of the effects on the parent drug, tramadol, and the active metabolite, M1 [see Warnings and Precautions (5.7), Drug Interactions (7)].

1 INDICATIONS AND USAGE

CONZIP is indicated for the management of severe and persistent pain that requires an opioid analgesic and that cannot be adequately treated with alternative options, including immediate-release opioids.

Limitation of Use

- Because of the risks of addiction, abuse, misuse, overdose, and death, which can occur at any dosage or duration and persist over the course of therapy [see Warnings and Precautions (5.1)], reserve opioid analgesics, including CONZIP, for use in patients for whom alternative treatment options are ineffective, not tolerated, or would be otherwise inadequate to provide sufficient management of pain.
- CONZIP is not indicated as an as-needed (prn) analgesic.

2 DOSAGE AND ADMINISTRATION

2.1 Important Dosage and Administration Instructions

- CONZIP should be prescribed only by healthcare professionals who are knowledgeable about the use of extended-release/long-acting opioids and how to mitigate the associated risks.
- Do not use CONZIP concomitantly with other tramadol products [see Warnings and Precautions (5.7), (5.15)].
- Do not administer CONZIP at a dose exceeding 300 mg per day.
- Use the lowest effective dosage for the shortest duration of time consistent with individual patient treatment goals [see Warnings and Precautions (5)]. Because the risk of overdose increases as opioid doses increase, reserve titration to higher doses of CONZIP for patients in whom lower doses are insufficiently effective and in whom the expected benefits of using a higher dose opioid clearly outweigh the substantial risks.
- Initiate the dosing regimen for each patient individually, taking into account the patient's underlying cause and severity of pain, prior analgesic treatment and response, and risk factors for addiction, abuse, and misuse [see Warnings and Precautions (5.1)].
- Respiratory depression can occur at any time during opioid therapy, especially when initiating and following dosage increases with CONZIP. Consider this risk when selecting an initial dose and when making dose adjustments [see Warnings and Precautions (5.2)].
- CONZIP is administered orally once daily.
- Instruct patients to swallow CONZIP capsules whole, and to take it with liquid. Breaking, chewing, splitting, or dissolving CONZIP capsules will result in uncontrolled delivery of tramadol and can lead to overdose or death [see Warnings and Precautions (5.1)].
- CONZIP may be taken without regard to food. It is recommended that CONZIP be taken in a consistent manner [see Clinical Pharmacology (12.3)].

2.2 Patient Access to an Opioid Overdose Reversal Agent for the Emergency Treatment of Opioid Overdose

Inform patients and caregivers about opioid overdose reversal agents (e.g., naloxone, nalmefene). Discuss the importance of having access to an opioid overdose reversal agent, especially if the patient has risk factors for overdose (e.g., concomitant use of CNS depressants, a history of opioid use disorder, or prior opioid overdose) or if there are household members (including children) or other close contacts at risk for accidental ingestion or opioid overdose. The presence of risk factors for overdose should not prevent the management of pain in any patient [see Warnings and Precautions (5.1, 5.2, 5.3)].

Discuss the options for obtaining an opioid overdose reversal agent (e.g., prescription, over-the-counter, or as part of a community-based program) [see Warnings and Precautions (5.2)].

There are important differences among the opioid overdose reversal agents, such as route of administration, product strength, approved patient age range, and pharmacokinetics. Be familiar with these differences, as outlined in the approved labeling for those products, prior to recommending or prescribing such an agent.

2.3 Initial Dosage

It is safer to underestimate a patient's 24-hour tramadol requirements and provide rescue medication (e.g., immediate-release opioid) than to overestimate the 24-hour tramadol dosage and manage an adverse reaction due to an overdose. While useful tables of opioid equivalents are readily available, there is inter-patient variability in the potency of opioid drugs and opioid formulations. Frequently reevaluate patients for signs and symptoms of opioid withdrawal and for signs of oversedation/toxicity after converting patients to CONZIP.

Use of CONZIP

The initial dose of CONZIP is 100 mg once daily.

Patients Currently on Tramadol Immediate-Release (IR) Products

Calculate the 24-hour tramadol IR dose and initiate a total daily dose of CONZIP rounded down to the next lowest 100 mg increment. The dose should be taken once daily. The dose may subsequently be individualized according to patient need.

Due to limitations in flexibility of dose selection with CONZIP, some patients maintained on tramadol IR products may not be able to convert to CONZIP.

Conversion from Other Opioid Analgesics to CONZIP

When CONZIP therapy is initiated, discontinue all opioid analgesics other than those used on an as needed basis for breakthrough pain when appropriate. There are no established conversion ratios for conversion from other opioids to CONZIP defined by clinical trials. Initiate dosing using CONZIP 100 mg once a day.

2.4 Titration and Maintenance Therapy

Individually titrate CONZIP by 100 mg every five days to a dose that provides adequate analgesia and minimizes adverse reactions. The maximum daily dose of CONZIP is 300 mg per day.

Continually reevaluate patients receiving CONZIP to assess the maintenance of pain control, signs and symptoms of opioid withdrawal, and other adverse reactions, as well as to reassess for the development of addiction, abuse, or misuse [see Warnings and Precautions (5.1, 5.18)]. Frequent communication is important among the prescriber, other members of the healthcare team, the patient, and the caregiver/family during periods of changing analgesic requirements, including initial titration. During use of opioid therapy for an extended period of time, periodically reassess the continued need for the use of opioid analgesics.

Patients who experience breakthrough pain may require a dosage adjustment of CONZIP or may need rescue medication with an appropriate dose of an immediate-release analgesic. If the level of pain increases after dosage stabilization, attempt to identify the source of increased pain before increasing the CONZIP dosage.

If the level of pain increases after dosage stabilization, attempt to identify the source of increased pain before increasing the CONZIP dosage. If after increasing the dosage, unacceptable opioid-related adverse reactions are observed (including an increase in pain after a dosage increase), consider reducing the dosage [see Warnings and Precautions (5)]. Adjust the dosage to obtain an appropriate balance between management of pain and opioid-related adverse reactions.

2.5 Safe Reduction or Discontinuation of CONZIP

Do not rapidly reduce or abruptly discontinue CONZIP in patients who may be physically dependent on opioids. Rapid reduction or abrupt discontinuation of opioid analgesics in patients who are physically dependent on opioids has resulted in serious withdrawal symptoms, uncontrolled pain, and suicide. Rapid reduction or abrupt discontinuation has also been associated with attempts to find other sources of opioid analgesics, which may be confused with drug-seeking for abuse. Patients may also attempt to treat their pain or withdrawal symptoms with illicit opioids, such as heroin, and other substances.

When a decision has been made to decrease the dose or discontinue therapy in an opioid-dependent patient taking CONZIP, there are a variety of factors that should be considered, including the total daily dose of opioid (including CONZIP) the patient has been taking, the duration of treatment, the type of pain being treated, and the physical and psychological attributes of the patient. It is important to ensure ongoing care of the patient and to agree on an appropriate tapering schedule and follow-up plan so that patient and provider goals and expectations are clear and realistic. When opioid analgesics are being discontinued due to a suspected substance use disorder, evaluate and treat the patient, or refer for evaluation and treatment of the substance use disorder. Treatment should include evidence-based approaches, such as medication assisted treatment of opioid use disorder. Complex patients with comorbid pain and substance use disorders may benefit from referral to a specialist.

There are no standard opioid tapering schedules that are suitable for all patients. Good clinical practice dictates a patient-specific plan to taper the dose of the opioid gradually. For patients on CONZIP who are physically opioid-dependent, initiate the taper by a small enough increment (e.g., no greater than 10% to 25% of the total daily dose) to avoid withdrawal symptoms, and proceed with dose-lowering at an interval of every 2 to 4 weeks. Patients who have been taking opioids for briefer periods of time may tolerate a more rapid taper.

It may be necessary to provide the patient with lower dosage strengths to accomplish a successful taper. Reassess the patient frequently to manage pain and withdrawal symptoms, should they emerge. Common withdrawal symptoms include restlessness, lacrimation, rhinorrhea, yawning, perspiration, chills, myalgia, and mydriasis. Other signs and symptoms also may develop, including irritability, anxiety, backache, joint pain, weakness, abdominal cramps, insomnia, nausea, anorexia, vomiting, diarrhea, or increased blood pressure, respiratory rate, or heart rate. If withdrawal symptoms arise, it may be necessary to pause the taper for a period of time or raise the dose of the opioid analgesic to the previous dose, and then proceed with a slower taper. In addition, evaluate patients for any changes in mood, emergence of suicidal thoughts, or use of other substances.

When managing patients taking opioid analgesics, particularly those who have been treated for an extended period of time and/or with high doses for chronic pain, ensure that a multimodal approach to pain management, including mental health support (if needed), is in place prior to initiating an opioid analgesic taper. A multimodal approach to pain management may optimize the treatment of chronic pain, as well as assist with the successful tapering of the opioid analgesic [see Warnings and Precautions (5.18), Drug Abuse and Dependence (9.3)].

3 DOSAGE FORMS AND STRENGTHS

Extended-release capsules are available as:

100 mg Capsules: White capsule imprinted with blue ink "G 252" on cap and "100" between lines on the body
200 mg Capsules: White capsule imprinted with violet ink "G 253" on cap and "200" between lines on the body
300 mg Capsules: White capsule imprinted with red ink "G 254" on cap and "300" between lines on the body

4 CONTRAINDICATIONS

CONZIP is contraindicated for:

- All children younger than 12 years of age [see Warnings and Precautions (5.6)]
- Postoperative management in children younger than 18 years of age following tonsillectomy and/or adenoidectomy [see Warnings and Precautions (5.6)]

CONZIP is also contraindicated in patients with:

- Significant respiratory depression [see Warnings and Precautions (5.12)]
- Acute or severe bronchial asthma in an unmonitored setting or in the absence of resuscitative equipment [see Warnings and Precautions (5.12)]
- Known or suspected gastrointestinal obstruction, including paralytic ileus [see Warnings and Precautions (5.16)]
- Hypersensitivity to tramadol (e.g., anaphylaxis) [see Warnings and Precautions (5.17), Adverse Reactions (6)]
- Concurrent use of monoamine oxidase inhibitors (MAOIs) or use within the last 14 days [see Drug Interactions (7)]

5 WARNINGS AND PRECAUTIONS

5.1 Addiction, Abuse, and Misuse

CONZIP contains tramadol, a Schedule IV controlled substance. As an opioid, CONZIP exposes users to the risks of addiction, abuse and misuse.

Although the risk of addiction in any individual is unknown, it can occur in patients appropriately prescribed CONZIP. Addiction can occur at recommended dosages and if the drug is misused or abused. The risk of opioid-related overdose or overdose-related death is increased with higher opioid doses, and this risk persists over the course of therapy. In postmarketing studies, addiction, abuse, misuse, and fatal and non-fatal opioid overdose were observed in patients with long-term opioid use [see Adverse Reactions (6.2)].

Assess each patient's risk for opioid addiction, abuse, or misuse prior to prescribing CONZIP, and reassess all patients receiving CONZIP for the development of these behaviors and conditions. Risks are increased in patients with a personal or family history of substance abuse (including drug or alcohol abuse or addiction) or mental illness (e.g., major depression). The potential for these risks should not, however, prevent the proper management of pain in any given patient. Patients at increased risk may be prescribed opioids such as CONZIP but use in such patients necessitates intensive counseling about the risks and proper use of CONZIP along with frequent reevaluation for signs of addiction, abuse, and misuse. Consider recommending or prescribing an opioid overdose reversal agent [see Dosage and Administration (2.2), Warnings and Precautions (5.2)].

Abuse or misuse of CONZIP by splitting, breaking, chewing, crushing, snorting, or injecting the dissolved product will result in the uncontrolled delivery of tramadol and can result in overdose and death [see Overdosage (10)].

Opioids are sought for nonmedical use and are subject to diversion from legitimate prescribed use. Consider these risks when prescribing or dispensing CONZIP. Strategies to reduce these risks include prescribing the drug in the smallest appropriate quantity and advising the patient on careful storage of the drug during the course of treatment and the proper disposal of unused drug. Contact local state professional licensing board or state-controlled substances authority for information on how to prevent and detect abuse or diversion of this product.

5.2 Life-Threatening Respiratory Depression

Serious, life-threatening, or fatal respiratory depression has been reported with the use of opioids, even when used as recommended. Respiratory depression, if not immediately recognized and treated, may lead to respiratory arrest and death. Management of respiratory depression may include close observation, supportive measures, and use of opioid overdose reversal agents, depending on the patient's clinical status [see Overdosage (10)]. Carbon dioxide (CO2) retention from opioid-induced respiratory depression can exacerbate the sedating effects of opioids.

While serious, life-threatening, or fatal respiratory depression can occur at any time during the use of CONZIP, the risk is greatest during the initiation of therapy or following a dosage increase.

To reduce the risk of respiratory depression, proper dosing and titration of CONZIP are essential [see Dosage and Administration (2)]. Overestimating the CONZIP dosage when converting patients from another opioid product can result in a fatal overdose with the first dose.

Accidental ingestion of even one dose of CONZIP, especially by children, can result in respiratory depression and death due to an overdose of tramadol.

Educate patients and caregivers on how to recognize respiratory depression and emphasize the importance of calling 911 or getting emergency medical help right away in the event of a known or suspected overdose.

Opioids can cause sleep-related breathing disorders including central sleep apnea (CSA) and sleep-related hypoxemia. Opioid use increases the risk of CSA in a dose-dependent fashion. In patients who present with CSA, consider decreasing the opioid dosage using best practices for opioid taper [see Dosage and Administration (2.5)].

Patient Access to an Opioid Overdose Reversal Agent for the Emergency Treatment of Opioid Overdose

Inform patients and caregivers about opioid overdose reversal agents (e.g., naloxone, nalmefene). Discuss the importance of having access to an opioid overdose reversal agent, especially if the patient has risk factors for overdose (e.g., concomitant use of CNS depressants, a history of opioid use disorder, or prior opioid overdose) or if there are household members (including children) or other close contacts at risk for accidental ingestion or opioid overdose. The presence of risk factors for overdose should not prevent the management of pain in any patient [see Warnings and Precautions (5.1, 5.3)].

Discuss the options for obtaining an opioid overdose reversal agent (e.g., prescription, over-the-counter, or as part of a community-based program).

There are important differences among the opioid overdose reversal agents, such as route of administration, product strength, approved patient age range, and pharmacokinetics. Be familiar with these differences, as outlined in the approved labeling for those products, prior to recommending or prescribing such an agent.

Educate patients and caregivers on how to recognize respiratory depression, and how to use an opioid overdose reversal agent for the emergency treatment of opioid overdose. Emphasize the importance of calling 911 or getting emergency medical help, even if an opioid overdose reversal agent is administered [see Dosage and Administration (2.2), Warnings and Precautions (5.1, 5.3), Overdosage (10)].

5.3 Risks from Concomitant Use with Benzodiazepines or Other CNS Depressants

Profound sedation, respiratory depression, coma, and death may result from the concomitant use of CONZIP with benzodiazepines and/or other CNS depressants, including alcohol (e.g., non-benzodiazepine sedatives/hypnotics, anxiolytics, tranquilizers, muscle relaxants, general anesthetics, antipsychotics, gabapentinoids [gabapentin and pregabalin], and other opioids). Because of these risks, reserve concomitant prescribing of these drugs for use in patients for whom alternative treatment options are inadequate.

Observational studies have demonstrated that concomitant use of opioid analgesics and benzodiazepines increases the risk of drug-related mortality compared to use of opioid analgesics alone. Because of similar pharmacological properties, it is reasonable to expect similar risk with the concomitant use of other CNS depressant drugs with opioid analgesics [see Drug Interactions (7)].

If the decision is made to prescribe a benzodiazepine or other CNS depressant concomitantly with an opioid analgesic, prescribe the lowest effective dosages and minimum durations of concomitant use. In patients already receiving an opioid analgesic, prescribe a lower initial dose of the benzodiazepine or other CNS depressant than indicated in the absence of an opioid, and titrate based on clinical response. If an opioid analgesic is initiated in a patient already taking a benzodiazepine or other CNS depressant, prescribe a lower initial dose of the opioid analgesic, and titrate based on clinical response. Inform patients and caregivers of this potential interaction and educate them on the signs and symptoms of respiratory depression (including sedation). If concomitant use is warranted, consider recommending or prescribing an opioid overdose reversal agent [see Dosage and Administration (2.2), Warnings and Precautions (5.2), Overdosage (10)].

Advise both patients and caregivers about the risks of respiratory depression and sedation when CONZIP is used with benzodiazepines or other CNS depressants (including alcohol and illicit drugs). Advise patients not to drive or operate heavy machinery until the effects of concomitant use of the benzodiazepine or other CNS depressants have been determined. Screen patients for risk of substance use disorders, including opioid abuse and misuse, and warn them of the risk for overdose and death associated with the use of additional CNS depressants including alcohol and illicit drugs [see Drug Interactions (7)].

5.4 Neonatal Opioid Withdrawal Syndrome

Use of CONZIP for an extended period of time during pregnancy can result in withdrawal in the neonate. Neonatal opioid withdrawal syndrome, unlike opioid withdrawal syndrome in adults, may be life-threatening if not recognized and treated, and requires management according to protocols developed by neonatology experts. Observe newborns for signs of neonatal opioid withdrawal syndrome and manage accordingly. Advise pregnant women using opioids for an extended period of time of the risk of neonatal opioid withdrawal syndrome and ensure that appropriate treatment will be available [see Use in Specific Populations (8.1)].

5.5 Opioid Analgesic Risk Evaluation and Mitigation Strategy (REMS)

To ensure that the benefits of opioid analgesics outweigh the risks of addiction, abuse, and misuse, the Food and Drug Administration (FDA) has required a Risk Evaluation and Mitigation Strategy (REMS) for these products. Under the requirements of the REMS, drug companies with approved opioid analgesic products must make REMS-compliant education programs available to healthcare providers. Healthcare providers are strongly encouraged to do all of the following:

- Complete a REMS-compliant education program offered by an accredited provider of continuing education (CE) or another education program that includes all the elements of the FDA Education Blueprint for Healthcare Providers Involved in the Management or Support of Patients with Pain.
- Discuss the safe use, serious risks, and proper storage and disposal of opioid analgesics with patients and/or their caregivers every time these medicines are prescribed. The Patient Counseling Guide (PCG) can be obtained at this link: www.fda.gov/OpioidAnalgesicREMSPCG.
- Emphasize to patients and their caregivers the importance of reading the Medication Guide that they will receive from their pharmacist every time an opioid analgesic is dispensed to them.
- Consider using other tools to improve patient, household, and community safety, such as patient-prescriber agreements that reinforce patient-prescriber responsibilities.

To obtain further information on the opioid analgesic REMS and for a list of accredited REMS CME/CE, call 1-800-503-0784, or log on to www.opioidanalgesicrems.com. The FDA Blueprint can be found at www.fda.gov/OpioidAnalgesicREMSBlueprint.

5.6 Ultra-Rapid Metabolism of Tramadol and Other Risk Factors for Life-Threatening Respiratory Depression in Children

Life-threatening respiratory depression and death have occurred in children who received tramadol. Tramadol and codeine are subject to variability in metabolism based upon CYP2D6 genotype (described below), which can lead to increased exposure to an active metabolite. Based upon postmarketing reports with tramadol or with codeine, children younger than 12 years of age may be more susceptible to the respiratory depressant effects of tramadol. Furthermore, children with obstructive sleep apnea who are treated with opioids for post-tonsillectomy and/or adenoidectomy pain may be particularly sensitive to their respiratory depressant effect. Because of the risk of life-threatening respiratory depression and death:

- CONZIP is contraindicated for all children younger than 12 years of age [see Contraindications (4)].
- CONZIP is contraindicated for post-operative management in pediatric patients younger than 18 years of age following tonsillectomy and/or adenoidectomy [see Contraindications (4)].
- Avoid the use of CONZIP in adolescents 12 to 18 years of age who have other risk factors that may increase their sensitivity to the respiratory depressant effects of tramadol unless the benefits outweigh the risks. Risk factors include conditions associated with hypoventilation, such as postoperative status, obstructive sleep apnea, obesity, severe pulmonary disease, neuromuscular disease, and concomitant use of other medications that cause respiratory depression.
- As with adults, when prescribing opioids for adolescents, healthcare providers should choose the lowest effective dose for the shortest period of time and inform patients and caregivers about these risks and the signs of opioid overdose [see Use in Specific Populations (8.4), Overdosage (10)].

Nursing Mothers

Tramadol is subject to the same polymorphic metabolism as codeine, with ultra-rapid metabolizers of CYP2D6 substrates being potentially exposed to life-threatening levels of O-desmethyltramadol (M1). At least one death was reported in a nursing infant who was exposed to high levels of morphine in breast milk because the mother was an ultra-rapid metabolizer of codeine. A baby nursing from an ultra-rapid metabolizer mother taking CONZIP could potentially be exposed to high levels of M1, and experience life-threatening respiratory depression. For this reason, breastfeeding is not recommended during treatment with CONZIP [see Use in Specific Populations (8.2)].

CYP2D6 Genetic Variability: Ultra-rapid metabolizer

Some individuals may be ultra-rapid metabolizers because of a specific CYP2D6 genotype (gene duplications denoted as *1/*1×N or *1/*2×N). The prevalence of this CYP2D6 phenotype varies widely and has been estimated at 1 to 10% for Whites (European, North American), 3 to 4% for Blacks (African Americans), 1 to 2% for East Asians (Chinese, Japanese, Korean), and may be greater than 10% in certain racial/ethnic groups (i.e., Oceanian, Northern African, Middle Eastern, Ashkenazi Jews, Puerto Rican).

These individuals convert tramadol into its active metabolite, O-desmethyltramadol (M1), more rapidly and completely than other people. This rapid conversion results in higher than expected serum M1 levels. Even at labeled dosage regimens, individuals who are ultra-rapid metabolizers may have life-threatening or fatal respiratory depression or experience signs of overdose (such as extreme sleepiness, confusion, or shallow breathing) [see Overdosage (10)]. Therefore, individuals who are ultra-rapid metabolizers should not use CONZIP.

5.7 Risks of Interactions with Drugs Affecting Cytochrome P450 Isoenzymes

The effects of concomitant use or discontinuation of cytochrome P450 3A4 inducers, 3A4 inhibitors, or 2D6 inhibitors on levels of tramadol and M1 from CONZIP are complex. Use of cytochrome P450 3A4 inducers, 3A4 inhibitors, or 2D6 inhibitors with CONZIP requires careful consideration of the effects on the parent drug, tramadol which is a weak serotonin and norepinephrine reuptake inhibitor and mu-opioid agonist, and the active metabolite, M1, which is more potent than tramadol in mu-opioid receptor binding [see Drug Interactions (7)].

Risks of Concomitant Use or Discontinuation of Cytochrome P450 2D6 Inhibitors

The concomitant use of CONZIP with all cytochrome P450 2D6 inhibitors (e.g., amiodarone, quinidine) may result in an increase in tramadol plasma levels and a decrease in the levels of the active metabolite, M1. A decrease in M1 exposure in patients who have developed physical dependence to tramadol, may result in signs and symptoms of opioid withdrawal and reduced efficacy. The effect of increased tramadol levels may be an increased risk for serious adverse events including seizures and serotonin syndrome.

Discontinuation of a concomitantly used cytochrome P450 2D6 inhibitor may result in a decrease in tramadol plasma levels and an increase in active metabolite M1 levels, which could increase or prolong adverse reactions related to opioid toxicity and may cause potentially fatal respiratory depression.

Evaluate patients receiving CONZIP and any CYP2D6 inhibitor at frequent intervals for the risk of serious adverse events including seizures and serotonin syndrome, signs and symptoms that may reflect opioid toxicity, and opioid withdrawal when CONZIP is used in conjunction with inhibitors of CYP2D6 [see Drug Interactions (7)].

Cytochrome P450 3A4 Interaction

The concomitant use of CONZIP with cytochrome P450 3A4 inhibitors, such as macrolide antibiotics (e.g., erythromycin), azole-antifungal agents (e.g., ketoconazole), and protease inhibitors (e.g., ritonavir) or discontinuation of a cytochrome P450 3A4 inducer such as rifampin, carbamazepine, and phenytoin, may result in an increase in tramadol plasma concentrations, which could increase or prolong adverse reactions, increase the risk for serious adverse events including seizures and serotonin syndrome, and may cause potentially fatal respiratory depression.

The concomitant use of CONZIP with all cytochrome P450 3A4 inducers or discontinuation of a cytochrome P450 3A4 inhibitor may result in lower tramadol levels. This may be associated with a decrease in efficacy, and in some patients, may result in signs and symptoms of opioid withdrawal.

Evaluate patients receiving CONZIP and any CYP3A4 inhibitor or inducer at frequent intervals for the risk for serious adverse events including seizures and serotonin syndrome, signs and symptoms that may reflect opioid toxicity and opioid withdrawal when CONZIP is used in conjunction with inhibitors and inducers of CYP3A4 [see Drug Interactions (7)].

5.8 Opioid-Induced Hyperalgesia and Allodynia

Opioid-Induced Hyperalgesia (OIH) occurs when an opioid analgesic paradoxically causes an increase in pain, or an increase in sensitivity to pain. This condition differs from tolerance, which is the need for increasing doses of opioids to maintain a defined effect [see Dependence (9.3)]. Symptoms of OIH include (but may not be limited to) increased levels of pain upon opioid dosage increase, decreased levels of pain upon opioid dosage decrease, or pain from ordinarily non-painful stimuli (allodynia). These symptoms may suggest OIH only if there is no evidence of underlying disease progression, opioid tolerance, opioid withdrawal, or addictive behavior.

Cases of OIH have been reported, both with short-term and longer-term use of opioid analgesics. Though the mechanism of OIH is not fully understood, multiple biochemical pathways have been implicated. Medical literature suggests a strong biologic plausibility between opioid analgesics and OIH and allodynia. If a patient is suspected to be experiencing OIH, carefully consider appropriately decreasing the dose of the current opioid analgesic or opioid rotation (safely switching the patient to a different opioid moiety) [see Dosage and Administration (2.5), Warnings and Precautions (5.18)].

5.9 Serotonin Syndrome Risk

Cases of serotonin syndrome, a potentially life-threatening condition, have been reported with the use of tramadol products, including CONZIP, particularly during concomitant use with serotonergic drugs. Serotonergic drugs include selective serotonin reuptake inhibitors (SSRIs), serotonin and norepinephrine reuptake inhibitors (SNRIs), tricyclic antidepressants (TCAs), triptans, 5-HT3 receptor antagonists, drugs that affect the serotonergic neurotransmitter system (e.g., mirtazapine, trazodone, tramadol), certain muscle relaxants (i.e., cyclobenzaprine, metaxalone), and drugs that impair metabolism of serotonin (including monoamine oxidase inhibitors, both those intended to treat psychiatric disorders and also others, such as linezolid and intravenous methylene blue) [see Drug Interactions (7)]. This may occur within the recommended dosage range.

Serotonin syndrome symptoms may include mental status changes (e.g., agitation, hallucinations, coma), autonomic instability (e.g., tachycardia, labile blood pressure, hyperthermia), neuromuscular aberrations (e.g., hyperreflexia, incoordination, rigidity), and/or gastrointestinal symptoms (e.g., nausea, vomiting, diarrhea). The onset of symptoms generally occurs within several hours to a few days of concomitant use but may occur later than that. Discontinue CONZIP if serotonin syndrome is suspected.

5.10 Increased Risk of Seizures

Seizures have been reported in patients receiving tramadol within the recommended dosage range. Spontaneous post-marketing reports indicate that seizure risk is increased with doses of tramadol above the recommended range.

Concomitant use of tramadol increases the seizure risk in patients taking: [see Drug Interactions (7)]

- Selective serotonin reuptake inhibitors (SSRIs) and serotonin-norepinephrine reuptake inhibitors (SNRIs) antidepressants or anorectics,
- Tricyclic antidepressants (TCAs), and other tricyclic compounds (e.g., cyclobenzaprine, promethazine, etc.),
- Other opioids,
- Monoamine oxidase inhibitors (MAOIs) [see Warnings and Precautions (5.9), Drug Interactions (7)],
- Neuroleptics, or
- Other drugs that reduce the seizure threshold.

Risk of seizures may also increase in patients with epilepsy, those with a history of seizures, or in patients with a recognized risk for seizure (such as head trauma, metabolic disorders, alcohol and drug withdrawal, CNS infections).

In tramadol overdose, administration of an opioid overdose reversal agent (e.g., naloxone or nalmefene) may increase the risk of seizure.

5.11 Suicide Risk

- Do not prescribe CONZIP for patients who are suicidal or addiction-prone. Consideration should be given to the use of non-narcotic analgesics in patients who are suicidal or depressed [see Drug Abuse and Dependence (9.2)].
- Prescribe CONZIP with caution for patients with a history of misuse and/or who are currently taking CNS-active drugs including tranquilizers or antidepressant drugs, or alcohol in excess, and patients who suffer from emotional disturbance or depression [see Drug Interactions (7)].
- Inform patients not to exceed the recommended dose and to limit their intake of alcohol [see Dosage and Administration (2.1), Warnings and Precautions (5.3)].

5.12 Life-Threatening Respiratory Depression in Patients with Chronic Pulmonary Disease or in Elderly, Cachectic, or Debilitated Patients

The use of CONZIP in patients with acute or severe bronchial asthma in an unmonitored setting or in the absence of resuscitative equipment is contraindicated.

Patients with Chronic Pulmonary Disease: CONZIP treated patients with significant chronic obstructive pulmonary disease or cor pulmonale, and those with a substantially decreased respiratory reserve, hypoxia, hypercapnia, or pre-existing respiratory depression are at increased risk of decreased respiratory drive including apnea, even at recommended dosages of CONZIP [see Warnings and Precautions (5.2)].

Elderly, Cachectic, or Debilitated Patients: Life-threatening respiratory depression is more likely to occur in elderly, cachectic, or debilitated patients because they may have altered pharmacokinetics or altered clearance compared to younger, healthier patients [see Warnings and Precautions (5.2)].

Regularly evaluate patients, particularly when initiating and titrating CONZIP and when CONZIP is given concomitantly with other drugs that depress respiration [see Warnings and Precautions (5.2, 5.7)]. Alternatively, consider the use of non-opioid analgesics in these patients.

5.13 Adrenal Insufficiency

Cases of adrenal insufficiency have been reported with opioid use, more often following greater than one month of use. Presentation of adrenal insufficiency may include non-specific symptoms and signs including nausea, vomiting, anorexia, fatigue, weakness, dizziness, and low blood pressure. If adrenal insufficiency is suspected, confirm the diagnosis with diagnostic testing as soon as possible. If adrenal insufficiency is diagnosed, treat with physiologic replacement doses of corticosteroids. Wean the patient off of the opioid to allow adrenal function to recover and continue corticosteroid treatment until adrenal function recovers. Other opioids may be tried as some cases reported use of a different opioid without recurrence of adrenal insufficiency. The information available does not identify any particular opioids as being more likely to be associated with adrenal insufficiency.

5.14 Severe Hypotension

CONZIP may cause severe hypotension including orthostatic hypotension and syncope in ambulatory patients. There is increased risk in patients whose ability to maintain blood pressure has already been compromised by a reduced blood volume or concurrent administration of certain CNS depressant drugs (e.g., phenothiazines or general anesthetics) [see Drug Interactions (7)]. Regularly evaluate these patients for signs of hypotension after initiating or titrating the dosage of CONZIP. In patients with circulatory shock, CONZIP may cause vasodilation that can further reduce cardiac output and blood pressure. Avoid the use of CONZIP in patients with circulatory shock.

5.15 Risks of Use in Patients with Increased Intracranial Pressure, Brain Tumors, Head Injury, or Impaired Consciousness

In patients who may be susceptible to the intracranial effects of CO2 retention (e.g., those with evidence of increased intracranial pressure or brain tumors), CONZIP may reduce respiratory drive, and the resultant CO2 retention can further increase intracranial pressure. Monitor such patients for signs of sedation and respiratory depression, particularly when initiating therapy with CONZIP.

Opioids may also obscure the clinical course in a patient with a head injury. Avoid the use of CONZIP in patients with impaired consciousness or coma.

5.16 Risks of Gastrointestinal Complications

CONZIP is contraindicated in patients with known or suspected gastrointestinal obstruction, including paralytic ileus.

The tramadol in CONZIP may cause spasm of the sphincter of Oddi. Opioids may cause increases in serum amylase. Regularly evaluate patients with biliary tract disease, including acute pancreatitis, for worsening symptoms.

Cases of opioid-induced esophageal dysfunction (OIED) have been reported in patients taking opioids. The risk of OIED may increase as the dose and/or duration of opioids increases. Regularly evaluate patients for signs and symptoms of OIED (e.g., dysphagia, regurgitation, non-cardiac chest pain), and if necessary, adjust opioid therapy as clinically appropriate. [see Clinical Pharmacology (12.2)].

5.17 Anaphylaxis and Other Hypersensitivity Reactions

Serious and rarely fatal hypersensitive reactions have been reported in patients receiving therapy with tramadol. When these events do occur, it is often following the first dose. Other reported hypersensitivity reactions include pruritus, hives, bronchospasm, angioedema, toxic epidermal necrolysis and Stevens-Johnson syndrome. Patients with a history of hypersensitivity reactions to tramadol and other opioids may be at increased risk and therefore should not receive CONZIP. If anaphylaxis or other hypersensitivity occurs, stop administration of CONZIP immediately, discontinue CONZIP permanently, and do not rechallenge with any formulation of tramadol. Advise patients to seek immediate medical attention if they experience any symptoms of a hypersensitivity reaction [see Contraindications (4)].

5.18 Withdrawal

Do not rapidly reduce or abruptly discontinue CONZIP in a patient physically dependent on opioids. When discontinuing CONZIP in a physically-dependent patient, gradually taper the dosage. Rapid tapering of tramadol in a patient physically dependent on opioids may lead to a withdrawal syndrome and return of pain [see Dosage and Administration (2.5), Drug Abuse and Dependence (9.3)].

Additionally, avoid the use of mixed agonist/antagonist (e.g., pentazocine, nalbuphine, and butorphanol) or partial agonist (e.g., buprenorphine) analgesics in patients who are receiving a full opioid agonist analgesic, including CONZIP. In these patients, mixed agonist/antagonist and partial agonist analgesics may reduce the analgesic effect and/or may precipitate withdrawal symptoms [see Drug Interactions (7)].

When discontinuing CONZIP, gradually taper the dosage [see Dosage and Administration (2.5)]. Do not abruptly discontinue CONZIP [see Drug Abuse and Dependence (9.3)].

5.19 Risks of Driving and Operating Machinery

CONZIP may impair the mental or physical abilities needed to perform potentially hazardous activities such as driving a car or operating machinery. Warn patients not to drive or operate dangerous machinery unless they are tolerant to the effects of CONZIP and know how they will react to the medication.

5.20 Hyponatremia

Hyponatremia (serum sodium <135 mmol/L) has been reported with the use of tramadol, and many cases are severe (sodium level <120 mmol/L). Most cases of hyponatremia occurred in females over the age of 65 and within the first week of therapy. In some reports, hyponatremia resulted from the syndrome of inappropriate antidiuretic hormone secretion (SIADH). Assess patients for signs and symptoms of hyponatremia (e.g., confusion, disorientation) during treatment with CONZIP, especially during initiation of therapy. If signs and symptoms of hyponatremia are present, initiate appropriate treatment (e.g., fluid restriction) and discontinue CONZIP [see Dosage and Administration (2.5)].

5.21 Hypoglycemia

Cases of tramadol-associated hypoglycemia have been reported, some resulting in hospitalization. In most cases, patients had predisposing risk factors (e.g., diabetes). If hypoglycemia is suspected, monitor blood glucose levels and consider drug discontinuation as appropriate [see Dosage and Administration (2.5)].

6 ADVERSE REACTIONS

The following serious or otherwise important adverse reactions are described in greater detail, in other sections:

- Addiction, Abuse, and Misuse [see Warnings and Precautions (5.1)]
- Life-Threatening Respiratory Depression [see Warnings and Precautions (5.2)]
- Interactions with Benzodiazepines and Other CNS Depressants [see Warnings and Precautions (5.3)]
- Neonatal Opioid Withdrawal Syndrome [see Warnings and Precautions (5.4)]
- Ultra-Rapid Metabolism of Tramadol and Other Risk Factors for Life-Threatening Respiratory Depression in Children [see Warnings and Precautions (5.6)]
- Opioid-Induced Hyperalgesia and Allodynia [see Warnings and Precautions (5.8)]
- Serotonin Syndrome [see Warnings and Precautions (5.9)]
- Seizures [see Warnings and Precautions (5.10)]
- Suicide [see Warnings and Precautions (5.11)]
- Adrenal Insufficiency [see Warnings and Precautions (5.13)]
- Severe Hypotension [see Warnings and Precautions (5.14)]
- Gastrointestinal Adverse Reactions [see Warnings and Precautions (5.16)]
- Hypersensitivity Reactions [see Warnings and Precautions (5.17)]
- Withdrawal [see Warnings and Precautions (5.18)]

6.1 Clinical Trials Experience

Because clinical trials are conducted under widely varying conditions, adverse reaction rates observed in the clinical trials of a drug cannot be directly compared to rates in the clinical trials of another drug and may not reflect the rates observed in practice.

CONZIP capsules were administered to a total of 1987 patients in clinical trials. These included four double-blind and one long-term, open-label study in patients with osteoarthritis of the hip and knee. A total of 812 patients were 65 years or older. Adverse reactions with doses from 100 mg to 300 mg in the four pooled, randomized, double-blind, placebo-controlled studies in patients with chronic non-malignant pain are presented in the following table (see Table 1).

Table 1: Incidence (%) of Patients with Adverse Reaction Rates ≥5% from Four Double-Blind, Placebo-Controlled Studies in Patients with Moderate to Moderately Severe Chronic Pain by Dose (N=1917)
 | CONZIP |  |  | Placebo
Preferred Term | 100 mg (N=429) n (%) | 200 mg (N=434) n (%) | 300 mg (N=1054) n (%) | (N=646) n (%)
Headache | 99 (23.1) | 96 (22.1) | 200 (19.0) | 128 (19.8)
Nausea | 69 (16.1) | 93 (21.4) | 265 (25.1) | 37 (5.7)
Somnolence | 50 (11.7) | 60 (13.8) | 170 (16.1) | 26 (4.0)
Dizziness | 41 (9.6) | 54 (12.4) | 143 (13.6) | 31 (4.8)
Constipation | 40 (9.3) | 59 (13.6) | 225 (21.3) | 27 (4.2)
Vomiting | 28 (6.5) | 45 (10.4) | 98 (9.3) | 12 (1.9)
Arthralgia | 23 (5.4) | 20 (4.6) | 53 (5.0) | 33 (5.1)
Dry Mouth | 20 (4.7) | 36 (8.3) | 138 (13.1) | 22 (3.4)
Sweating | 18 (4.2) | 23 (5.3) | 71 (6.7) | 4 (0.6)
Asthenia | 15 (3.5) | 26 (6.0) | 91 (8.6) | 17 (2.6)
Pruritus | 13 (3.0) | 25 (5.8) | 77 (7.3) | 12 (1.9)
Anorexia | 9 (2.1) | 23 (5.3) | 60 (5.7) | 1 (0.2)
Insomnia | 9 (2.1) | 9 (2.1) | 53 (5.0) | 11 (1.7)

The following adverse reactions were reported from all chronic pain studies (N=1917). The lists below include adverse reactions not otherwise noted in Table 1.

Adverse reactions with incidence rates of 1.0% to <5.0%

Cardiac disorders: hypertension
Gastrointestinal disorders: dyspepsia, flatulence
General disorders: abdominal pain, accidental injury, chills, fever, flu syndrome, neck pain, pelvic pain
Investigations: hyperglycemia, urine abnormality
Metabolism and nutrition disorders: peripheral edema, weight loss
Musculoskeletal, connective tissue and bone disorders: myalgia
Nervous system disorders: paresthesia, tremor, withdrawal syndrome
Psychiatric disorders: agitation, anxiety, apathy, confusion, depersonalization, depression, euphoria, nervousness
Respiratory, thoracic and mediastinal disorders: bronchitis, pharyngitis, rhinitis, sinusitis
Skin and subcutaneous tissue disorders: rash
Urogenital disorders: prostatic disorder, urinary tract infection
Vascular disorders: vasodilatation

Adverse reactions with incidence rates of 0.5% to <1.0% at any dose and serious adverse reactions reported in at least two patients

Cardiac disorders: EKG abnormal, hypotension, tachycardia
Gastrointestinal disorders: gastroenteritis
General disorders: neck rigidity, viral infection
Hematologic/Lymphatic disorders: anemia, ecchymoses
Metabolism and nutrition disorders: blood urea nitrogen increased, GGT increased, gout, SGPT increased
Musculoskeletal disorders: arthritis, arthrosis, joint disorder, leg cramps
Nervous system disorders: emotional lability, hyperkinesia, hypertonia, thinking abnormal, twitching, vertigo
Respiratory disorders: pneumonia
Skin and subcutaneous tissue disorders: hair disorder, skin disorder, urticaria
Special Senses: eye disorder, lacrimation disorder
Urogenital disorders: cystitis, dysuria, sexual function abnormality, urinary retention

6.2 Postmarketing Experience

The following adverse reactions have been identified during post approval use of tramadol. Because these reactions are reported voluntarily from a population of uncertain size, it is not always possible to reliably estimate their frequency or establish a causal relationship to drug exposure.

Serotonin syndrome: Cases of serotonin syndrome, a potentially life-threatening condition, have been reported during concomitant use of opioids with serotonergic drugs.

Adrenal insufficiency: Cases of adrenal insufficiency have been reported with opioid use, more often following greater than one month of use.

Anaphylaxis: Anaphylaxis has been reported with ingredients contained in CONZIP.

Androgen deficiency: Cases of androgen deficiency have occurred with use of opioids for an extended period of time [see Clinical Pharmacology (12.2)].

Hyperalgesia and Allodynia: Cases of hyperalgesia and allodynia have been reported with opioid therapy of any duration [see Warnings and Precautions (5.8)].

QT prolongation/torsade de pointes: Cases of QT prolongation and/or torsade de pointes have been reported with tramadol use. Many of these cases were reported in patients taking another drug labeled for QT prolongation, in patients with a risk factor for QT prolongation (e.g., hypokalemia), or in overdose setting.

Metabolism and nutrition disorders

Hyponatremia: Cases of severe hyponatremia and/or SIADH have been reported in patients taking tramadol, most often in females over the age of 65, and within the first week of therapy [see Warnings and Precautions (5.20)].

Hypoglycemia: Cases of hypoglycemia have been reported in patients taking tramadol. Most reports were in patients with predisposing risk factors, including diabetes or renal insufficiency, or in elderly patients [see Warnings and Precautions (5.21)].

Opioid-induced esophageal dysfunction (OIED): Cases of OIED have been reported in patients taking opioids, and may occur more frequently in patients taking higher doses of opioid, and/or in patients taking opioids longer term [see Warnings and Precautions (5.16)].

Adverse Reactions from Observational Studies

A prospective, observational cohort study estimated the risks of addiction, abuse, and misuse in patients initiating long-term use of Schedule II opioid analgesics between 2017 and 2021. Study participants included in one or more analyses had been enrolled in selected insurance plans or health systems for at least one year, were free of at least one outcome at baseline, completed a minimum number of follow-up assessments, and either: 1) filled multiple extended-release/long-acting opioid analgesic prescriptions during a 90 day period (n=978); or 2) filled any Schedule II opioid analgesic prescriptions covering at least 70 of 90 days (n=1,244). Those included also had no dispensing of the qualifying opioids in the previous 6 months.

Over 12 months:

- approximately 1% to 6% of participants across the two cohorts newly met criteria for addiction, as assessed with two validated interview-based measures of moderate-to-severe opioid use disorder based on Diagnostic and Statistical Manual of Mental Disorders, Fifth Edition (DSM-5) criteria, and
- approximately 9% and 22% of participants across the two cohorts newly met criteria for prescription opioid abuse and misuse [defined in Drug Abuse and Dependence (9.2)], respectively, as measured with a validated self-reported instrument.

A retrospective, observational cohort study estimated the risk of opioid-involved overdose or opioid overdose-related death in patients with new long-term use of Schedule II opioid analgesics from 2006 through 2016 (n=220,249). Included patients had been enrolled in either one of two commercial insurance programs, one managed care program, or one Medicaid program for at least 9 months. New long-term use was defined as having Schedule II opioid analgesic prescriptions covering at least 70 days' supply over the 3 months prior to study entry and none during the preceding 6 months. Patients were excluded if they had an opioid-involved overdose in the 9 months prior to study entry. Overdose was measured using a validated medical code-based algorithm with linkage to the National Death Index database. The 5-year cumulative incidence estimates for opioid-involved overdose or opioid overdose-related death ranged from approximately 1.5% to 4% across study sites, counting only the first event during follow-up. Approximately 17% of first opioid overdoses observed over the entire study period (5-11 years, depending on the study site) were fatal. Higher baseline opioid dose was the strongest and most consistent predictor of opioid-involved overdose or opioid overdose-related death. Study exclusion criteria may have selected patients at lower risk of overdose, and substantial loss to follow-up (approximately 80%) also may have biased estimates.

The risk estimates from the studies described above may not be generalizable to all patients receiving opioid analgesics, such as those with exposures shorter or longer than the duration evaluated in the studies.

7 DRUG INTERACTIONS

Table 2 includes clinically significant drug interactions with CONZIP.

Table 2: Clinically Significant Drug Interactions with CONZIP
Inhibitors of CYP2D6
Clinical Impact: | The concomitant use of CONZIP and CYP2D6 inhibitors may result in an increase in the plasma concentration of tramadol and a decrease in the plasma concentration of M1, particularly when an inhibitor is added after a stable dose of CONZIP is achieved. Since M1 is a more potent mu-opioid agonist, decreased M1 exposure could result in decreased therapeutic effects, and may result in signs and symptoms of opioid withdrawal in patients who had developed physical dependence to tramadol. Increased tramadol exposure can result in increased or prolonged therapeutic effects and increased risk for serious adverse events including seizures and serotonin syndrome.
Clinical Impact: | After stopping a CYP2D6 inhibitor, as the effects of the inhibitor decline, the tramadol plasma concentration will decrease and the M1 plasma concentration will increase which could increase or prolong therapeutic effects but also increase adverse reactions related to opioid toxicity, and may cause potentially fatal respiratory depression [see Clinical Pharmacology (12.3)].
Intervention: | If concomitant use of a CYP2D6 inhibitor is necessary, evaluate patients at frequent intervals for adverse reactions including opioid withdrawal, seizures, and serotonin syndrome.
Intervention: | If a CYP2D6 inhibitor is discontinued, consider lowering CONZIP dosage until stable drug effects are achieved. Evaluate patients at frequent intervals for adverse events including respiratory depression and sedation.
Examples: | Quinidine, fluoxetine, paroxetine, and bupropion
Inhibitors of CYP3A4
Clinical Impact: | The concomitant use of CONZIP and CYP3A4 inhibitors can increase the plasma concentration of tramadol and may result in a greater amount of metabolism via CYP2D6 and greater levels of M1. Follow patients closely for increased risk of serious adverse events including seizures and serotonin syndrome, and adverse reactions related to opioid toxicity including potentially fatal respiratory depression, particularly when an inhibitor is added after a stable dose of CONZIP is achieved.
Clinical Impact: | After stopping a CYP3A4 inhibitor, as the effects of the inhibitor decline, the tramadol plasma concentration will decrease [see Clinical Pharmacology (12.3)], resulting in decreased opioid efficacy and possibly signs and symptoms of opioid withdrawal in patients who had developed physical dependence to tramadol.
Intervention: | If concomitant use is necessary, consider dosage reduction of CONZIP until stable drug effects are achieved. Evaluate patients at frequent intervals for seizures and serotonin syndrome, and signs of respiratory depression and sedation.
Intervention: | If a CYP3A4 inhibitor is discontinued, consider increasing the CONZIP dosage until stable drug effects are achieved and evaluate patients for signs and symptoms of opioid withdrawal.
Examples: | Macrolide antibiotics (e.g., erythromycin), azole-antifungal agents (e.g., ketoconazole), protease inhibitors (e.g., ritonavir)
CYP3A4 Inducers
Clinical Impact: | The concomitant use of CONZIP and CYP3A4 inducers can decrease the plasma concentration of tramadol [see Clinical Pharmacology (12.3)], resulting in decreased efficacy or onset of a withdrawal syndrome in patients who have developed physical dependence to tramadol [see Warnings and Precautions (5.7)].
Clinical Impact: | After stopping a CYP3A4 inducer, as the effects of the inducer decline, the tramadol plasma concentration will increase [see Clinical Pharmacology (12.3)], which could increase or prolong both the therapeutic effects and adverse reactions and may cause seizures and serotonin syndrome, and potentially fatal respiratory depression.
Intervention: | If concomitant use is necessary, consider increasing the CONZIP dosage until stable drug effects are achieved. Evaluate patients for signs of opioid withdrawal.
Intervention: | If a CYP3A4 inducer is discontinued, consider CONZIP dosage reduction and evaluate patients at frequent intervals for seizures and serotonin syndrome, and signs of respiratory depression and sedation.
Intervention: | Patients taking carbamazepine, a CYP3A4 inducer, may have a significantly reduced analgesic effect of tramadol. Because carbamazepine increases tramadol metabolism and because of the seizure risk associated with tramadol, concomitant administration of CONZIP and carbamazepine is not recommended.
Examples: | Rifampin, carbamazepine, phenytoin
Benzodiazepines and Other Central Nervous System (CNS) Depressants
Clinical Impact: | Due to additive pharmacologic effect, the concomitant use of benzodiazepines or other CNS depressants, including alcohol, can increase the risk of hypotension, respiratory depression, profound sedation, coma, and death [see Warnings and Precautions (5.3)].
Intervention: | Reserve concomitant prescribing of these drugs for use in patients for whom alternative treatment options are inadequate. Limit dosages and durations to the minimum required. Inform patients and caregivers of this potential interaction and educate them on the signs and symptoms of respiratory depression (including sedation). If concomitant use is warranted, consider recommending or prescribing an opioid overdose reversal agent [see Dosage and Administration (2.2), Warnings and Precautions (5.1, 5.2, 5.3)].
Examples: | Benzodiazepines and other sedatives/hypnotics, anxiolytics, tranquilizers, muscle relaxants, general anesthetics, antipsychotics, gabapentinoids (gabapentin or pregabalin), other opioids, alcohol
Serotonergic Drugs
Clinical Impact: | The concomitant use of opioids with other drugs that affect the serotonergic neurotransmitter system has resulted in serotonin syndrome [see Warnings and Precautions (5.9)].
Intervention: | If concomitant use is warranted, frequently evaluate the patient, particularly during treatment initiation and dose adjustment. Discontinue CONZIP if serotonin syndrome is suspected.
Examples: | Selective serotonin reuptake inhibitors (SSRIs), serotonin and norepinephrine reuptake inhibitors (SNRIs), tricyclic antidepressants (TCAs), triptans, 5-HT3 receptor antagonists, drugs that affect the serotonin neurotransmitter system (e.g., mirtazapine, trazodone, tramadol), certain muscle relaxants (i.e., cyclobenzaprine, metaxalone), monoamine oxidase inhibitors (those intended to treat psychiatric disorders and also others, such as linezolid and intravenous methylene blue)
Monoamine Oxidase Inhibitors (MAOIs)
Clinical Impact: | MAOI interactions with opioids may manifest as serotonin syndrome [see Warnings and Precautions (5.9)] or opioid toxicity (e.g., respiratory depression, coma) [see Warnings and Precautions (5.2)].
Intervention: | Do not use CONZIP in patients taking MAOIs or within 14 days of stopping such treatment.
Examples: | Phenelzine, tranylcypromine, linezolid
Mixed Agonist/Antagonist and Partial Agonist Opioid Analgesics
Clinical Impact: | May reduce the analgesic effect of CONZIP and/or precipitate withdrawal symptoms.
Intervention: | Avoid concomitant use.
Examples: | Butorphanol, nalbuphine, pentazocine, buprenorphine
Muscle Relaxants
Clinical Impact: | Tramadol may enhance the neuromuscular blocking action of skeletal muscle relaxants and produce an increased degree of respiratory depression.
Intervention: | Because respiratory depression may be greater than otherwise expected, decrease the dosage of CONZIP and/or the muscle relaxant as necessary. Due to the risk of respiratory depression with concomitant use of skeletal muscle relaxants and opioids, consider recommending or prescribing an opioid overdose reversal agent [see Dosage and Administration (2.2), Warnings and Precautions (5.2)].
Examples: | Cyclobenzaprine, metaxalone.
Diuretics
Clinical Impact: | Opioids can reduce the efficacy of diuretics by inducing the release of antidiuretic hormone.
Intervention: | Evaluate patients for signs of diminished diuresis and/or effects on blood pressure and increase the dosage of the diuretic as needed.
Anticholinergic Drugs
Clinical Impact: | The concomitant use of anticholinergic drugs may increase risk of urinary retention and/or severe constipation, which may lead to paralytic ileus.
Intervention: | Evaluate patients for signs of urinary retention or reduced gastric motility when CONZIP is used concomitantly with anticholinergic drugs.
Digoxin
Clinical Impact: | Post-marketing surveillance of tramadol has revealed rare reports of digoxin toxicity.
Intervention: | Evaluate patients at frequent intervals for signs of digoxin toxicity and adjust dosage of digoxin as needed.
Warfarin
Clinical Impact: | Post-marketing surveillance of tramadol has revealed rare reports of alteration of warfarin effect, including elevation of prothrombin times.
Intervention: | Frequently reevaluate the prothrombin time of patients on warfarin for signs of an interaction and adjust the dosage of warfarin as needed.

8 USE IN SPECIFIC POPULATIONS

8.1 Pregnancy

Risk Summary

Use of opioid analgesics for an extended period of time during pregnancy may cause neonatal opioid withdrawal syndrome [see Warnings and Precautions (5.4)]. Available data with CONZIP in pregnant women are insufficient to inform a drug-associated risk for major birth defects and miscarriage.

In animal reproduction studies, tramadol administration during organogenesis decreased fetal weights and reduced ossification in mice, rats, and rabbits at 1.4, 0.6, and 3.6 times the maximum recommended human daily dosage (MRHD). Tramadol decreased pup body weight and increased pup mortality at 1.2 and 1.9 times the MRHD [see Data]. Based on animal data, advise pregnant women of the potential risk to a fetus.

The background risk of major birth defects and miscarriage for the indicated population is unknown. All pregnancies have a background risk of birth defect, loss, or other adverse outcomes. In the U.S. general population, the estimated background risk of major birth defects and miscarriage in clinically recognized pregnancies is 2 to 4% and 15 to 20%, respectively.

Clinical Considerations

Fetal/Neonatal Adverse Reactions

Use of opioid analgesics for an extended period of time during pregnancy for medical or nonmedical purposes can result in physical dependence in the neonate and neonatal opioid withdrawal syndrome shortly after birth. Neonatal opioid withdrawal syndrome presents as irritability, hyperactivity and abnormal sleep pattern, high pitched cry, tremor, vomiting, diarrhea, and failure to gain weight. The onset, duration, and severity of neonatal opioid withdrawal syndrome vary based on the specific opioid used, duration of use, timing and amount of last maternal use, and rate of elimination of the drug by the newborn. Observe newborns for symptoms of neonatal opioid withdrawal syndrome and manage accordingly [see Warnings and Precautions (5.4)].

Neonatal seizures, neonatal withdrawal syndrome, fetal death and still birth have been reported with tramadol during post-approval use of tramadol immediate-release products.

Labor or Delivery

Opioids cross the placenta and may produce respiratory depression and psycho-physiologic effects in neonates. An opioid overdose reversal agent, such as naloxone or nalmefene, must be available for reversal of opioid-induced respiratory depression in the neonate. CONZIP is not recommended for use in pregnant women during or immediately prior to labor, when use of shorter-acting analgesics or other analgesic techniques are more appropriate. Opioid analgesics, including CONZIP can prolong labor through actions which temporarily reduce the strength, duration, and frequency of uterine contractions. However, this effect is not consistent and may be offset by an increased rate of cervical dilation, which tends to shorten labor. Monitor neonates exposed to opioid analgesics during labor for signs of excess sedation and respiratory depression.

Tramadol has been shown to cross the placenta. The mean ratio of serum tramadol in the umbilical veins compared to maternal veins was 0.83 for 40 women given tramadol during labor.

The effect of CONZIP, if any, on the later growth, development, and functional maturation of the child is unknown.

Data

Animal Data

Tramadol has been shown to be embryotoxic and fetotoxic in mice, (120 mg/kg), rats (25 mg/kg) and rabbits (75 mg/kg) at maternally toxic dosages but was not teratogenic at these dose levels. These doses on a mg/m^2 basis are 1.9, 0.8, and 4.9 times the maximum recommended human daily dosage (MRHD) for mouse, rat and rabbit, respectively.

No drug-related teratogenic effects were observed in progeny of mice (up to 140 mg/kg), rats (up to 80 mg/kg) or rabbits (up to 300 mg/kg) treated with tramadol by various routes. Embryo and fetal toxicity consisted primarily of decreased fetal weights, decreased skeletal ossification, and increased supernumerary ribs at maternally toxic dose levels. Transient delays in developmental or behavioral parameters were also seen in pups from rat dams allowed to deliver. Embryo and fetal lethality were reported only in one rabbit study at 300 mg/kg, a dose that would cause extreme maternal toxicity in the rabbit. The dosages listed for mouse, rat, and rabbit are 2.3, 2.6, and 19 times the MRHD, respectively.

Tramadol was evaluated in pre- and post-natal studies in rats. Progeny of dams receiving oral (gavage) dose levels of 50 mg/kg (1.6 times the MRHD) or greater had decreased weights, and pup survival was decreased early in lactation at 80 mg/kg (2.6 times the MRHD).

8.2 Lactation

Risk Summary

CONZIP is not recommended for obstetrical preoperative medication or for post-delivery analgesia in nursing mothers because its safety in infants and newborns has not been studied.

Tramadol and its metabolite, O-desmethyltramadol (M1), are present in human milk. There is no information on the effects of the drug on the breastfed infant or the effects of the drug on milk production. The M1 metabolite is more potent than tramadol in mu-opioid receptor binding [see Clinical Pharmacology (12.1)]. Published studies have reported tramadol and M1 in colostrum with administration of tramadol to nursing mothers in the early post-partum period. Women who are ultra-rapid metabolizers of tramadol may have higher than expected serum levels of M1, potentially leading to higher levels of M1 in breast milk that can be dangerous in their breastfed infants. In women with normal tramadol metabolism, the amount of tramadol secreted into human milk is low and dose dependent. Because of the potential for serious adverse reactions, including excess sedation and respiratory depression in a breastfed infant, advise patients that breastfeeding is not recommended during treatment with CONZIP.

Clinical Considerations

Monitor infants exposed to CONZIP through breast milk for excess sedation and respiratory depression. Withdrawal symptoms can occur in breastfed infants when maternal administration of an opioid analgesic is stopped, or when breast-feeding is stopped.

Data

Following a single IV 100 mg dose of tramadol, the cumulative excretion in breast milk within 16 hours post dose was 100 mcg of tramadol (0.1% of the maternal dose) and 27 mcg of M1.

8.3 Females and Males of Reproductive Potential

Infertility

Use of opioids for an extended period of time may cause reduced fertility in females and males of reproductive potential. It is not known whether these effects on fertility are reversible [see Adverse Reactions (6.2), Clinical Pharmacology (12.2), Nonclinical Toxicology (13.1)].

8.4 Pediatric Use

The safety and effectiveness of CONZIP in pediatric patients have not been established.

Life-threatening respiratory depression and death have occurred in children who received tramadol [see Warnings and Precautions (5.6)]. In some of the reported cases, these events followed tonsillectomy and/or adenoidectomy, and one of the children had evidence of being an ultra-rapid metabolizer of tramadol (i.e., multiple copies of the gene for cytochrome P450 isoenzyme 2D6). Children with sleep apnea may be particularly sensitive to the respiratory depressant effects of tramadol. Because of the risk of life-threatening respiratory depression and death:

- CONZIP is contraindicated for all children younger than 12 years of age [see Contraindications (4)].
- CONZIP is contraindicated for post-operative management in pediatric patients younger than 18 years of age following tonsillectomy and/or adenoidectomy [see Contraindications (4)].
- Avoid the use of CONZIP in adolescents 12 to 18 years of age who have other risk factors that may increase their sensitivity to the respiratory depressant effects of tramadol unless the benefits outweigh the risks. Risk factors include conditions associated with hypoventilation, such as postoperative status, obstructive sleep apnea, obesity, severe pulmonary disease, neuromuscular disease, and concomitant use of other medications that cause respiratory depression [see Warnings and Precautions (5.6)].

8.5 Geriatric Use

Eight hundred and twelve elderly (65 years of age or older) subjects were exposed to CONZIP in clinical trials. Of those subjects, two hundred and forty were 75 years of age and older. In general, higher incidence rates of adverse events were observed for patients older than 65 years of age compared with patients 65 years and younger, particularly for the following adverse events: nausea, constipation, somnolence, dizziness, dry mouth, vomiting, asthenia, pruritus, anorexia, sweating, fatigue, weakness, postural hypotension and dyspepsia. For this reason, CONZIP should be used with great caution in patients older than 75 years of age [see Dosage and Administration (2.3)].

Respiratory depression is the chief risk for elderly patients treated with opioids and has occurred after large initial doses were administered to patients who were not opioid-tolerant or when opioids were co-administered with other agents that depress respiration. Titrate the dosage of CONZIP slowly in geriatric patients and frequently reevaluate the patient for signs of central nervous system and respiratory depression [see Warnings and Precautions (5.12)].

Tramadol is known to be substantially excreted by the kidney, and the risk of adverse reactions to this drug may be greater in patients with impaired renal function. Because elderly patients are more likely to have decreased renal function, care should be taken in dose selection, and it may be useful to regularly evaluate renal function.

8.6 Hepatic Impairment

Metabolism of tramadol and M1 is reduced in patients with advanced cirrhosis of the liver. CONZIP has not been studied in patients with hepatic impairment. The limited availability of dose strengths of CONZIP does not permit the dosing flexibility required for safe use in patients with severe hepatic impairment (Child-Pugh Class C). Therefore, CONZIP should not be used in patients with severe hepatic impairment [see Clinical Pharmacology (12.3)].

8.7 Renal Impairment

CONZIP has not been studied in patients with renal impairment. Impaired renal function results in a decreased rate and extent of excretion of tramadol and its active metabolite, M1. The limited availability of dose strengths of CONZIP does not permit the dosing flexibility required for safe use in patients with severe renal impairment (Child-Pugh Class C). Therefore, CONZIP should not be used in patients with severe renal impairment [see Clinical Pharmacology (12.3)].

9 DRUG ABUSE AND DEPENDENCE

9.1 Controlled Substance

CONZIP contains tramadol, a Schedule IV controlled substance.

9.2 Abuse

CONZIP contains tramadol, a substance with potential for misuse and abuse, which can lead to the development of substance use disorder, including addiction [see Warnings and Precautions (5.1)].

Misuse is the intentional use, for therapeutic purposes, of a drug by an individual in a way other than prescribed by a healthcare provider or for whom it was not prescribed.

Abuse is the intentional, non-therapeutic use of a drug, even once, for its desirable psychological or physiological effects.

Drug addiction is a cluster of behavioral, cognitive, and physiological phenomena that may include a strong desire to take the drug, difficulties in controlling drug use (e.g., continuing drug use despite harmful consequences, giving a higher priority to drug use than other activities and obligations), and possible tolerance or physical dependence.

Misuse and abuse of CONZIP increases risk of overdose, which may lead to central nervous system and respiratory depression, hypotension, seizures, and death. The risk is increased with concurrent abuse of CONZIP with alcohol and/or other CNS depressants. Abuse of and addiction to opioids in some individuals may not be accompanied by concurrent tolerance and symptoms of physical dependence. In addition, abuse of opioids can occur in the absence of addiction.

All patients treated with opioids require careful and frequent reevaluation for signs of misuse, abuse, and addiction, because use of opioid analgesic products carries the risk of addiction even under appropriate medical use. Patients at high risk of CONZIP abuse include those with a history of prolonged use of any opioid, including products containing tramadol, those with a history of drug or alcohol abuse, or those who use CONZIP in combination with other abused drugs.

"Drug-seeking" behavior is very common in persons with substance use disorders. Drug-seeking tactics include emergency calls or visits near the end of office hours, refusal to undergo appropriate examination, testing, or referral, repeated "loss" of prescriptions, tampering with prescriptions, and reluctance to provide prior medical records or contact information for other treating healthcare provider(s). "Doctor shopping" (visiting multiple prescribers to obtain additional prescriptions) is common among people who abuse drugs and people with substance use disorder. Preoccupation with achieving adequate pain relief can be appropriate behavior in a patient with inadequate pain control.

CONZIP, like other opioids, can be diverted for nonmedical use into illicit channels of distribution. Careful record-keeping of prescribing information, including quantity, frequency, and renewal requests, as required by state and federal law, is strongly advised.

Proper assessment of the patient, proper prescribing practices, periodic reevaluation of therapy, and proper dispensing and storage are appropriate measures that help to limit abuse of opioid drugs.

Risks Specific to Abuse of CONZIP

Abuse of CONZIP poses a risk of overdose and death. This risk is increased with concurrent use of CONZIP with alcohol and/or other CNS depressants [see Warnings and Precautions (5.1, 5.3), Drug Interactions (7)].

CONZIP is approved for oral use only. With parental abuse, the inactive ingredients in CONZIP can result in local tissue necrosis, infection, pulmonary granulomas, increased risk of endocarditis and valvular heart injury, embolism, and death.

Parenteral drug abuse is commonly associated with transmission of infectious diseases such as hepatitis and HIV.

9.3 Dependence

Both tolerance and physical dependence can develop during use of opioid therapy.

Tolerance is a physiological state characterized by a reduced response to a drug after repeated administration (i.e., a higher dose of a drug is required to produce the same effect that was once obtained at a lower dose).

Physical dependence is a state that develops as a result of a physiological adaptation in response to repeated drug use, manifested by withdrawal signs and symptoms after abrupt discontinuation or a significant dose reduction of a drug.

Withdrawal may be precipitated through the administration of drugs with opioid antagonist activity (e.g., naloxone, nalmefene), mixed agonist/antagonist analgesics (e.g., pentazocine, butorphanol, nalbuphine), or partial agonists (e.g., buprenorphine). Physical dependence may not occur to a clinically significant degree until after several days to weeks of continued use.

Do not rapidly reduce or abruptly discontinue CONZIP in a patient physically dependent on opioids. Rapid tapering of CONZIP in a patient physically dependent on opioids may lead to serious withdrawal symptoms, uncontrolled pain, and suicide. Rapid discontinuation has also been associated with attempts to find other sources of opioid analgesics, which may be confused with drug-seeking for abuse.

When discontinuing CONZIP, gradually taper the dosage using a patient-specific plan that considers the following: the dose of CONZIP the patient has been taking, the duration of treatment, and the physical and psychological attributes of the patient. To improve the likelihood of a successful taper and minimize withdrawal symptoms, it is important that the opioid tapering schedule is agreed upon by the patient. In patients taking opioids for an extended period of time at high doses, ensure that a multimodal approach to pain management, including mental health support (if needed), is in place prior to initiating an opioid analgesic taper [see Dosage and Administration (2.5), Warnings and Precautions (5.18)].

Infants born to mothers physically dependent on opioids will also be physically dependent and may exhibit respiratory difficulties and withdrawal signs [see Use in Specific Populations (8.1)].

10 OVERDOSAGE

Clinical Presentation

Acute overdosage with tramadol can be manifested by respiratory depression, somnolence progressing to stupor or coma, skeletal muscle flaccidity, cold and clammy skin, constricted pupils, and, in some cases, pulmonary edema, bradycardia, QT prolongation, hypotension, partial or complete airway obstruction, atypical snoring, and death. Marked mydriasis rather than miosis may be seen with hypoxia in overdose situations. [see Clinical Pharmacology (12.2)]. Toxic leukoencephalopathy has been reported after opioid overdose and can present hours, days, or weeks after apparent recovery from the initial intoxication.

Treatment of Overdose

In case of overdosage, priorities are the reestablishment of a patent and protected airway and institution of assisted or controlled ventilation, if needed. Employ other supportive measures (including oxygen and vasopressors) in the management of circulatory shock and pulmonary edema as indicated. Cardiac arrest or arrhythmias will require advanced life-support measures.

For clinically significant respiratory or circulatory depression secondary to opioid overdose, administer an opioid overdose reversal agent such as naloxone or nalmefene.

While an opioid overdose reversal agent will reverse some, but not all, symptoms caused by overdosage with tramadol, the risk of seizures is also increased with reversal agent administration. In animals, convulsions following the administration of toxic doses of CONZIP could be suppressed with barbiturates or benzodiazepines but were increased with naloxone. Naloxone administration did not change the lethality of an overdose in mice. Hemodialysis is not expected to be helpful in an overdose because it removes less than 7% of the administered dose in a 4-hour dialysis period.

Because the duration of opioid reversal is expected to be less than the duration of action of tramadol in CONZIP, carefully monitor the patient until spontaneous respiration is reliably reestablished. CONZIP will continue to release tramadol and add to the tramadol load for 24 to 48 hours or longer following ingestion, necessitating prolonged monitoring. If the response to an opioid overdose reversal agent is suboptimal or only brief in nature, administer additional reversal agent as directed by the product's prescribing information.

In an individual physically dependent on opioids, administration of the recommended usual dosage of the opioid overdose reversal agent will precipitate an acute withdrawal syndrome. The severity of the withdrawal symptoms experienced will depend on the degree of physical dependence and the dose of the reversal agent administered. If a decision is made to treat serious respiratory depression in the physically dependent patient, administration of the reversal agent should be initiated with care and by titration with smaller than usual doses of the reversal agent.

11 DESCRIPTION

CONZIP (tramadol hydrochloride) is an opioid agonist in an extended-release oral formulation. The chemical name for tramadol hydrochloride USP is (±)cis-2-[(dimethylamino)methyl]-1-(3-methoxyphenyl) cyclohexanol hydrochloride. Its structural formula is:

Figure 1

C16 H25 NO2 . HCl

The molecular weight of tramadol hydrochloride USP is 299.8. It is a white, bitter, crystalline and odorless powder that is readily soluble in water and ethanol and has a pKa of 9.41. The n-octanol/water log partition coefficient (logP) is 1.35 at pH 7.

CONZIP capsules contain a total dose of tramadol hydrochloride 100, 200, and 300 mg in a combination of immediate-release and extended-release components.

Dosage | Immediate-release | Extended-release
100 mg | 25 mg | 75 mg
200 mg | 50 mg | 150 mg
300 mg | 50 mg | 250 mg

CONZIP capsules are white in color. Inactive ingredients include gelatin, titanium dioxide, shellac, FD & C Blue #2 aluminum lake (E132) (100 and 200 mg capsules), D & C Red #7 calcium lake (E180) (200 and 300 mg capsules), D & C Yellow #10 aluminum lake (300 mg capsule), lactose monohydrate 200 mesh, microcrystalline cellulose, povidone K30, corn starch, sodium starch glycolate, magnesium stearate, sucrose stearate, hypromellose, talc, polysorbate 80, Eudragit NE 30D, and simethicone emulsion.

12 CLINICAL PHARMACOLOGY

12.1 Mechanism of Action

CONZIP contains tramadol, an opioid agonist, and an inhibitor of reuptake of norepinephrine and serotonin. Although its mode of action is not completely understood, from animal tests, at least two complementary mechanisms appear applicable: binding of parent and M1 metabolite to mu-opioid receptors and weak inhibition of reuptake of norepinephrine and serotonin.

Opioid activity of tramadol is due to both low affinity binding of the parent compound and higher affinity binding of the O-demethylated metabolite M1 to mu-opioid receptors. In animal models, M1 is up to 6 times more potent than tramadol in producing analgesia and 200 times more potent in mu-opioid binding. Tramadol-induced analgesia is only partially antagonized by the opioid antagonist naloxone in several animal tests. The relative contribution of both tramadol and M1 to human analgesia is dependent upon the plasma concentrations of each compound.

Tramadol has been shown to inhibit reuptake of norepinephrine and serotonin in vitro, as have some other opioid analgesics. These mechanisms may contribute independently to the overall analgesic profile of tramadol. The relationship between exposure of tramadol and M1 and efficacy has not been evaluated in clinical studies.

Apart from analgesia, tramadol administration may produce a constellation of symptoms (including dizziness, somnolence, nausea, constipation, sweating and pruritus) similar to that of other opioids. In contrast to morphine, tramadol has not been shown to cause histamine release. At therapeutic doses, tramadol has no effect on heart rate, left ventricular function or cardiac index. Orthostatic hypotension has been observed.

12.2 Pharmacodynamics

Effects on the Central Nervous System

Tramadol produces respiratory depression by direct action on brain stem respiratory centers. The respiratory depression involves a reduction in the responsiveness of the brain stem respiratory centers to both increases in carbon dioxide tension and electrical stimulation.

Tramadol causes miosis, even in total darkness. Pinpoint pupils are a sign of opioid overdose but are not pathognomonic (e.g., pontine lesions of hemorrhagic or ischemic origins may produce similar findings). Marked mydriasis rather than miosis may be seen due to hypoxia in overdose situations.

Effects on the Gastrointestinal Tract and Other Smooth Muscle

Tramadol causes a reduction in motility associated with an increase in smooth muscle tone in the antrum of the stomach and duodenum. Digestion of food in the small intestine is delayed and propulsive contractions are decreased. Propulsive peristaltic waves in the colon are decreased, while tone is increased to the point of spasm, resulting in constipation. Other opioid-induced effects may include a reduction in biliary and pancreatic secretions, spasm of sphincter of Oddi, transient elevations in serum amylase, and opioid-induced esophageal dysfunction (OIED).

Effects on the Cardiovascular System

Tramadol produces peripheral vasodilation, which may result in orthostatic hypotension or syncope. Manifestations of histamine release and/or peripheral vasodilation may include pruritus, flushing, red eyes, sweating, and/or orthostatic hypotension.

The effect of oral tramadol on the QTcF interval was evaluated in a double-blind, randomized, four-way crossover, placebo- and positive- (moxifloxacin) controlled study in 68 adult male and female healthy subjects. At a 600 mg/day dose (1.5-fold the maximum immediate-release daily dose), the study demonstrated no significant effect on the QTcF interval.

Effects on the Endocrine System

Opioids inhibit the secretion of adrenocorticotropic hormone (ACTH), cortisol, and luteinizing hormone (LH) in humans [see Adverse Reactions (6.2)]. They also stimulate prolactin, growth hormone (GH) secretion, and pancreatic secretion of insulin and glucagon.

Use of opioids for an extended period of time may influence the hypothalamic-pituitary-gonadal axis, leading to androgen deficiency that may manifest as low libido, impotence, erectile dysfunction, amenorrhea, or infertility. The causal role of opioids in the clinical syndrome of hypogonadism is unknown because the various medical, physical, lifestyle, and psychological stressors that may influence gonadal hormone levels have not been adequately controlled for in studies conducted to date [see Adverse Reactions (6.2)].

Effects on the Immune System

Opioids have been shown to have a variety of effects on components of the immune system in in vitro and animal models. The clinical significance of these findings is unknown. Overall, the effects of opioids appear to be modestly immunosuppressive.

Concentration–Efficacy Relationships

The minimum effective analgesic concentration will vary widely among patients, especially among patients who have been previously treated with opioid agonists. The minimum effective analgesic concentration of tramadol for any individual patient may increase over time due to an increase in pain, the development of a new pain syndrome, and/or the development of analgesic tolerance [see Dosage and Administration (2.1, 2.4)].

Concentration–Adverse Reaction Relationships

There is a relationship between increasing tramadol plasma concentration and increasing frequency of dose-related opioid adverse reactions such as nausea, vomiting, CNS effects, and respiratory depression. In opioid-tolerant patients, the situation may be altered by the development of tolerance to opioid-related adverse reactions [see Dosage and Administration (2.1, 2.3, 2.4)].

12.3 Pharmacokinetics

The analgesic activity of tramadol is due to both parent drug and the M1 metabolite. CONZIP is administered as a racemate and both tramadol and M1 are detected in the circulation. The Cmax and AUC of CONZIP capsules have been observed to be dose-proportional over an oral dose range of 100 to 300 mg in healthy subjects.

Absorption

After a single dose administration of CONZIP, Tmax occurs around 10-12 hours.

The mean Cmax and AUC of CONZIP capsules after a 300 mg single dose was 308 ng/mL and 6777 ng.hr/mL, respectively under fasting conditions. CONZIP is bioequivalent to a reference extended-release tramadol product following a single 300 mg dose under fasting conditions.

At steady-state, CONZIP at 200 mg has been observed to be bioequivalent to a reference extended-release tramadol product at 200 mg under fasting conditions (Table 3). Following administration of CONZIP 200 mg capsules, steady-state plasma concentrations of both tramadol and M1 are achieved within four days of once daily dosing.

Table 3
Mean (%CV) Steady-State Pharmacokinetic Parameter Values (N= 38)
Parameter | Tramadol |  | O-Desmethyltramadol (M1 Metabolite)
Parameter | Tramadol hydrochloride Extended- Release Capsules 200 mg | A Reference Extended-Release Tramadol Product 200 mg | Tramadol hydrochloride Extended-Release Capsules 200 mg | A Reference Extended-Release Tramadol Product 200 mg
AUC0-24 (ng.hr/mL) | 5678 (27%) | 5563 (32%) | 1319 (34%) | 1302 (40%)
Cmax (ng/mL) | 332 (25%) | 350 (31%) | 70 (34%) | 74 (41%)
Cmin (ng/mL) | 128 (39%) | 125 (45%) | 35 (34%) | 33 (42%)
Tmax | 5.9 (66%) | 10 (30%) | 11 (37%) | 13 (29%)
% Fluctuation | 88 (19%) | 101 (30%) | 64 (22%) | 76 (30%)
AUC0-24: Area Under the Curve in a 24-hour dosing interval
Cmax: Peak Concentration in a 24-hour dosing interval
Cmin: Trough Concentration in a 24-hour dosing interval
Tmax: Time to Peak Concentration

Food Effect

The rate and extent of absorption of CONZIP capsules (300 mg) are similar following oral administration with or without food. Therefore, CONZIP capsules can be administered without regard to meals.

Distribution

The volume of distribution of tramadol was 2.6 and 2.9 liters/kg in male and female subjects, respectively, following a 100 mg intravenous tramadol dose. The binding of tramadol to human plasma proteins is approximately 20% and binding also appears to be independent of concentration up to 10 mcg/mL. Saturation of plasma protein binding occurs only at concentrations outside the clinically relevant range.

Elimination

Tramadol is eliminated primarily through metabolism by the liver and the metabolites are eliminated primarily by the kidneys. The mean plasma elimination half-lives of racemic tramadol and racemic M1 after administration of CONZIP capsules are approximately 10 and 11 hours, respectively.

Metabolism

Tramadol is extensively metabolized after oral administration. The major metabolic pathways appear to be N- (mediated by CYP3A4 and CYP2B6) and O- (mediated by CYP2D6) demethylation and glucuronidation or sulfation in the liver. One metabolite (O-desmethyltramadol, denoted M1) is pharmacologically active in animal models. Formation of M1 is dependent on CYP2D6 and as such is subject to inhibition and polymorphism, which may affect the therapeutic response [see Drug Interactions (7)].

Excretion

Approximately 30% of the dose is excreted in the urine as unchanged drug, whereas 60% of the dose is excreted as metabolites. The remainder is excreted either as unidentified or as unextractable metabolites.

Special Populations

Hepatic Impairment

Pharmacokinetics of tramadol was studied in patients with mild or moderate hepatic impairment after receiving multiple doses of an extended-release tramadol product at 100 mg. The exposure of (+)- and (-)-tramadol was similar in mild and moderate hepatic impairment patients in comparison to patients with normal hepatic function. However, exposure of (+)- and (-)-M1 decreased ~50% with increased severity of the hepatic impairment (from normal to mild and moderate). The pharmacokinetics of tramadol has not been studied in patients with severe hepatic impairment. After the administration of tramadol immediate-release tablets to patients with advanced cirrhosis of the liver, tramadol area under the plasma concentration time curve was larger and the tramadol and M1 half-lives were longer than subjects with normal hepatic function. The limited availability of dose strengths of CONZIP does not permit the dosing flexibility required for safe use in patients with severe hepatic impairment. Therefore, CONZIP should not be used in patients with severe hepatic impairment [see Use in Specific Populations (8.6)].

Renal Impairment

Impaired renal function results in a decreased rate and extent of excretion of tramadol and its active metabolite, M1. The pharmacokinetics of tramadol was studied in patients with mild or moderate renal impairment after receiving multiple doses of an extended-release tramadol product at 100 mg. There is no consistent trend observed for tramadol exposure related to renal function in patients with mild (CLcr: 50-80 mL/min) or moderate (CLcr: 30-50 mL/min) renal impairment in comparison to patients with normal renal function (CLcr > 80 mL/min). However, exposure of M1 increased 20-40% with increased severity of the renal impairment (from normal to mild and moderate). The pharmacokinetics of tramadol has not been studied in patients with severe renal impairment (CLcr < 30 mL/min). The limited availability of dose strengths of CONZIP does not permit the dosing flexibility required for safe use in patients with severe renal impairment. Therefore, CONZIP should not be used in patients with severe renal impairment. The total amount of tramadol and M1 removed during a 4-hour dialysis period is less than 7% of the administered dose [see Use in Specific Populations (8.6)].

Sex

Based on pooled multiple-dose pharmacokinetics studies for an extended-release tramadol product in 166 healthy subjects (111 males and 55 females), the dose-normalized AUC values for tramadol were somewhat higher in females than in males. There was a considerable degree of overlap in values between male and female groups. Dosage adjustment based on sex is not recommended.

Age: Geriatric Population

The effect of age on pharmacokinetics of CONZIP has not been studied. Healthy elderly subjects aged 65 to 75 years administered an immediate-release formulation of tramadol, have plasma concentrations and elimination half-lives comparable to those observed in healthy subjects younger than 65 years of age. In subjects over 75 years, mean maximum plasma concentrations are elevated (208 vs. 162 ng/mL) and the mean elimination half-life is prolonged (7 vs. 6 hours) compared to subjects 65 to 75 years of age. Adjustment of the daily dose is recommended for patients older than 75 years [see Dosage and Administration (2.3)].

Drug Interaction Studies

Potential for Tramadol to Affect Other Drugs

In vitro studies indicate that tramadol is unlikely to inhibit the CYP3A4-mediated metabolism of other drugs when tramadol is administered concomitantly at therapeutic doses. Tramadol does not appear to induce its own metabolism in humans, since observed maximal plasma concentrations after multiple oral doses are higher than expected based on single-dose data.

Poor / Extensive Metabolizers, CYP2D6

The formation of the active metabolite, M1, is mediated by CYP2D6, a polymorphic enzyme. Approximately 7% of the population has reduced activity of the CYP2D6 isoenzyme of cytochrome P-450 metabolizing enzyme system. These individuals are "poor metabolizers" of debrisoquine, dextromethorphan and tricyclic antidepressants, among other drugs. Based on a population PK analysis of Phase 1 studies with IR tablets in healthy subjects, concentrations of tramadol were approximately 20% higher in "poor metabolizers" versus "extensive metabolizers", while M1 concentrations were 40% lower.

CYP2D6 Inhibitors

In vitro drug interaction studies in human liver microsomes indicate that concomitant administration with inhibitors of CYP2D6 such as fluoxetine, paroxetine, and amitriptyline could result in some inhibition of the metabolism of tramadol.

Quinidine

Tramadol is metabolized to active metabolite M1 by CYP2D6. Coadministration of quinidine, a selective inhibitor of CYP2D6, with tramadol ER resulted in a 50-60% increase in tramadol exposure and a 50-60% decrease in M1 exposure. The clinical consequences of these findings are unknown.

To evaluate the effect of tramadol, a CYP2D6 substrate on quinidine, an in vitro drug interaction study in human liver microsomes was conducted. The results from this study indicate that tramadol has no effect on quinidine metabolism [see Warnings and Precautions (5.1, 5.7), Drug Interactions (7)].

CYP3A4 Inhibitors and Inducers

Since tramadol is also metabolized by CYP3A4, administration of CYP3A4 inhibitors, such as ketoconazole and erythromycin, or CYP3A4 inducers, such as rifampin and St. John's Wort, with CONZIP may affect the metabolism of tramadol leading to altered tramadol exposure [see Warnings and Precautions (5.1, 5.7), Drug Interactions (7)].

Cimetidine

Concomitant administration of tramadol immediate-release tablets with cimetidine, a weak CPY3A4 inhibitor, does not result in clinically significant changes in tramadol pharmacokinetics. No alteration of the CONZIP dosage regimen with cimetidine is recommended.

Carbamazepine

Carbamazepine, a CYP3A4 inducer, increases tramadol metabolism. Patients taking carbamazepine may have a significantly reduced analgesic effect of tramadol. Concomitant administration of CONZIP and carbamazepine is not recommended.

13 NONCLINICAL TOXICOLOGY

13.1 Carcinogenesis, Mutagenesis, Impairment of Fertility

Carcinogenesis

Carcinogenicity assessment has been conducted in mice, rats and p53(+/-) heterozygous mice. A slight but statistically significant increase in two common murine tumors, pulmonary and hepatic, was observed in an NMRI mouse carcinogenicity study, particularly in aged mice. Mice were dosed orally up to 30 mg/kg in the drinking water (0.5 times the maximum recommended daily human dosage or MRHD) for approximately two years, although the study was not done with the Maximum Tolerated Dose. This finding is not believed to suggest risk in humans.

No evidence of carcinogenicity was noted in a rat 2-year carcinogenicity study testing oral doses of up to 30 mg/kg in the drinking water (1 times the MRHD). In a second rat study, no evidence of carcinogenicity was noted in rats at oral doses up to 75 mg/kg/day for males and 100 mg/kg/day for females (approximately 2 fold the maximum recommended human daily dose MRHD) for two years. However, the excessive decrease in body weight gain observed in the rat study might have reduced their sensitivity to any potential carcinogenic effect of the drug. No carcinogenic effect of tramadol was observed in p53(+/–)-heterozygous mice at oral doses up to 150 mg/kg/day for 26 weeks.

Mutagenesis

Tramadol was mutagenic in the presence of metabolic activation in the mouse lymphoma assay. Tramadol was not mutagenic in the in vitro bacterial reverse mutation assay using Salmonella and E. coli (Ames), the mouse lymphoma assay in the absence of metabolic activation, the in vitro chromosomal aberration assay, or the in vivo micronucleus assay in bone marrow.

Impairment of Fertility

No effects on fertility were observed for tramadol at oral dose levels up to 50 mg/kg in male rats and 75 mg/kg in female rats. These dosages are 1.2 and 1.8 times the maximum recommended human daily dose based on body surface area, respectively.

14 CLINICAL STUDIES

CONZIP is bioequivalent under fasting conditions to another extended-release tramadol product [see Clinical Pharmacology (12.3)] which demonstrated efficacy in two of four clinical trials of patients with chronic pain. To qualify for inclusion into these studies, patients were required to have moderate to moderately severe pain as defined by a pain intensity score of ≥40 mm, off previous medications, on a 0 - 100 mm visual analog scale (VAS).

In one 12-week randomized, double-blind, placebo-controlled study, patients with moderate to moderately severe pain due to osteoarthritis of the knee and/or hip were administered doses from 100 mg to 400 mg daily. Treatment with the extended-release tramadol product was initiated at 100 mg once daily for four days then increased by 100 mg per day increments every five days to the randomized fixed dose. Between 51% and 59% of patients in active treatment groups completed the study and 56% of patients in the placebo group completed the study. Discontinuations due to adverse events were more common in the extended-release tramadol product 200 mg, 300 mg and 400 mg treatment groups (20%, 27%, and 30% of discontinuations, respectively) compared to 14% of the patients treated with the extended-release tramadol product 100 mg and 10% of patients treated with placebo.

Pain, as assessed by the WOMAC Pain subscale, was measured at 1, 2, 3, 6, 9, and 12 weeks and change from baseline assessed. A responder analysis based on the percent change in WOMAC Pain subscale demonstrated a statistically significant improvement in pain for the 100 mg and 200 mg treatment groups compared to placebo (see Figure 2).

Figure 2

In one 12-week randomized, double-blind, placebo-controlled flexible-dosing trial of the extended-release tramadol product in patients with osteoarthritis of the knee, patients titrated to an average daily dose of approximately 270 mg/day. Forty-nine percent of patients randomized to the active treatment group completed the study, while 52% of patients randomized to placebo completed the study. Most of the early discontinuations in the active treatment group were due to adverse events, accounting for 27% of the early discontinuations in contrast to 7% of the discontinuations from the placebo group. Thirty-seven percent of the placebo-treated patients discontinued the study due to lack of efficacy compared to 15% of active-treated patients. The active treatment group demonstrated a statistically significant decrease in the mean Visual Analog Scale (VAS) score, and a statistically significant difference in the responder rate, based on the percent change from baseline in the VAS score, measured at 1, 2, 4, 8, and 12 weeks, between patients receiving the extended-release tramadol product and placebo (see Figure 3).

Figure 3

Four randomized, placebo-controlled clinical trials of CONZIP were conducted, none of which demonstrated efficacy but which differed in design from the preceding clinical studies described. Two trials were 12-week randomized placebo-controlled trials of CONZIP 100 mg/day, 200 mg/day, and 300 mg/day versus placebo in patients with moderate to moderately severe osteoarthritis pain of the hip and knee. The other two 12 week trials were similar in design, but only studied CONZIP 300 mg/day. In this fixed-dose design, subjects were required to titrate to a fixed dose, even if their pain responded to a lower titration dose.

16 HOW SUPPLIED/STORAGE AND HANDLING

CONZIP (tramadol hydrochloride) capsules are supplied as opaque white hard gelatin capsules, imprinted as follows.

100 mg Capsules: | White capsule imprinted with blue ink "G 252" on cap and "100" between lines on the body
Bottle of 30 capsules: | NDC 68025-071-30
200 mg Capsules: | White capsule imprinted with violet ink "G 253" on cap and "200" between lines on the body
Bottle of 30 capsules: | NDC 68025-072-30
300 mg Capsules: | White capsule imprinted with red ink "G 254" on cap and "300" between lines on the body
Bottle of 30 capsules: | NDC 68025-073-30

STORAGE AND HANDLING

Dispense in a tight container. Store at 20°C to 25°C (68°F to 77°F); excursions permitted to 15°C to 30°C (59°F to 86°F) [see USP Controlled Room Temperature]. Keep out of reach of children.

Store CONZIP securely and dispose of properly.

17 PATIENT COUNSELING INFORMATION

Advise the patient to read the FDA-approved patient labeling (Medication Guide)

Storage and Disposal

Because of the risks associated with accidental ingestion, misuse, and abuse, advise patients to store CONZIP securely, out of sight and reach of children, and in a location not accessible by others, including visitors to the home. Inform patients that leaving CONZIP unsecured can pose a deadly risk to others in the home [see Warnings and Precautions (5.1, 5.2), Drug Abuse and Dependence (9.2)].

Advise patients and caregivers that when medicines are no longer needed, they should be disposed of promptly. Inform patients that medicine take-back options are the preferred way to safely dispose of most types of unneeded medicines. If no take back programs or DEA-registered collectors are available, instruct patients to dispose of CONZIP by following these four steps:

- Mix CONZIP (do not crush) with an unpalatable substance such as dirt, cat litter, or used coffee grounds;
- Place the mixture in a container such as a sealed plastic bag;
- Throw the container in the household trash;
- Remove all personal information on the prescription label of the empty bottle

Inform patients that they can visit www.fda.gov/drugdisposal for additional information on disposal of unused medicines.

Addiction, Abuse, and Misuse

Inform patients that the use of CONZIP even when taken as recommended, can result in addiction, abuse, and misuse, which can lead to overdose and death [see Warnings and Precautions (5.1)]. Instruct patients not to share CONZIP with others and to take steps to protect CONZIP from theft or misuse.

Life-Threatening Respiratory Depression

Inform patients of the risk of life-threatening respiratory depression, including information that the risk is greatest when starting CONZIP or when the dosage is increased, and that it can occur even at recommended dosages.

Educate patients and caregivers on how to recognize respiratory depression and emphasize the importance of calling 911 or getting emergency medical help right away in the event of a known or suspected overdose [see Warnings and Precautions (5.2), Overdosage (10)].

Accidental Ingestion

Inform patients that accidental ingestion, especially by children, may result in respiratory depression or death [see Warnings and Precautions (5.2)]. Instruct patients to take steps to store CONZIP securely and to dispose of unused CONZIP in accordance with the local state guidelines and/or regulations.

Interactions with Benzodiazepines and Other CNS Depressants

Inform patients and caregivers that potentially fatal additive effects may occur if CONZIP is used with benzodiazepines or other CNS depressants, including alcohol (e.g., non-benzodiazepine sedative/hypnotics, anxiolytics, tranquilizers, muscle relaxants, general anesthetics, antipsychotics, gabapentinoids [gabapentin or pregabalin], and other opioids), and not to use these concomitantly unless supervised by a healthcare provider [see Warnings and Precautions (5.3), Drug Interactions (7)].

Patient Access to an Opioid Overdose Reversal Agent for the Emergency Treatment of Opioid Overdose

Inform patients and caregivers about opioid overdose reversal agents (e.g., naloxone, nalmefene). Discuss the importance of having access to an opioid overdose reversal agent, especially if the patient has risk factors for overdose (e.g., concomitant use of CNS depressants, a history of opioid use disorder, or prior opioid overdose) or if there are household members (including children) or other close contacts at risk for accidental ingestion or opioid overdose.

Discuss with the patient the options for obtaining an opioid overdose reversal agent (e.g., prescription, over-the-counter, or as part of a community-based program) [see Dosage and Administration (2.2), Warnings and Precautions (5.3)].

Educate patients and caregivers on how to recognize the signs and symptoms of an overdose.

Explain to patients and caregivers that effects of opioid overdose reversal agents like naloxone and nalmefene are temporary, and that they must call 911 or get emergency medical help right away in all cases of known or suspected opioid overdose, even if an opioid overdose reversal agent is administered [see Overdosage (10)].

Advise patients and caregivers:

- how to treat with the overdose reversal agent in the event of an opioid overdose.
- to tell family and friends about the opioid overdose reversal agent and to keep it in a place where family and friends can access it in an emergency.
- to read the Patient Information (or other educational material) that will come with the opioid overdose reversal agent. Emphasize the importance of doing this before an opioid emergency happens, so the patient and caregiver will know what to do.

Ultra-Rapid Metabolism of Tramadol and Other Risk Factors for Life-Threatening Respiratory Depression in Children

Advise caregivers that CONZIP is contraindicated in all children younger than 12 years of age and in children younger than 18 years of age following tonsillectomy and/or adenoidectomy. Advise caregivers of children ages 12 to 18 years of age receiving CONZIP to watch for signs of respiratory depression [see Warnings and Precautions (5.6)].

Hyperalgesia and Allodynia

Inform patients and caregivers not to increase opioid dosage without first consulting a clinician. Advise patients to seek medical attention if they experience symptoms of hyperalgesia, including worsening pain, increased sensitivity to pain, or new pain [see Warnings and Precautions (5.8), Adverse Reactions (6.2)].

Serotonin Syndrome

Inform patients that tramadol could cause a rare but potentially life-threatening condition called serotonin syndrome, particularly during concomitant use with serotonergic drugs. Warn patients of the symptoms of serotonin syndrome and to seek medical attention right away if symptoms develop. Instruct patients to inform their healthcare provider if they are taking, or plan to take serotonergic medications [see Warnings and Precautions (5.9), Drug Interactions (7)].

Seizures

Inform patients that CONZIP may cause seizures with concomitant use of serotonergic agents (including SSRIs, SNRIs, and triptans) or drugs that significantly reduce the metabolic clearance of tramadol [see Warnings and Precautions (5.10)].

MAOI Interaction

Inform patients not to take CONZIP while using any drugs that inhibit monoamine oxidase. Patients should not start MAOIs while taking CONZIP [see Drug Interactions (7)].

Important Administration Instructions

Instruct patients how to properly take CONZIP, including the following:

- CONZIP is designed to work properly only if swallowed intact. Taking cut, broken, chewed, crushed, or dissolved CONZIP tablets can result in a fatal overdose [see Dosage and Administration (2.1)].
- Advise patients not to exceed the single-dose and 24-hour dose limit and the time interval between doses, since exceeding these recommendations can result in respiratory depression, seizures, hepatic toxicity, and death.
- CONZIP should not be taken with alcohol containing beverages.

Important Discontinuation Instructions

In order to avoid developing withdrawal symptoms, instruct patients not to discontinue CONZIP without first discussing a tapering plan with the prescriber [see Dosage and Administration (2.5)].

Driving or Operating Heavy Machinery

Inform patients that CONZIP may impair the ability to perform potentially hazardous activities such as driving a car or operating heavy machinery. Advise patients not to perform such tasks until they know how they will react to the medication [see Warnings and Precautions (5.19)].

Constipation

Advise patients of the potential for severe constipation, including management instructions and when to seek medical attention [see Adverse Reactions (6), Clinical Pharmacology (12.1)].

Adrenal Insufficiency

Inform patients that CONZIP could cause adrenal insufficiency, a potentially life-threatening condition. Adrenal insufficiency may present with non-specific symptoms and signs such as nausea, vomiting, anorexia, fatigue, weakness, dizziness, and low blood pressure. Advise patients to seek medical attention if they experience a constellation of these symptoms [see Warnings and Precautions (5.13)].

Hypotension

Inform patients that CONZIP may cause orthostatic hypotension and syncope. Instruct patients how to recognize symptoms of low blood pressure and how to reduce the risk of serious consequences should hypotension occur (e.g., sit or lie down, carefully rise from a sitting or lying position) [see Warnings and Precautions (5.14)].

Anaphylaxis

Inform patients that anaphylaxis has been reported with ingredients contained in CONZIP. Advise patients how to recognize such a reaction and when to seek medical attention [see Contraindications (4), Adverse Reactions (6)].

Pregnancy

Neonatal Opioid Withdrawal Syndrome

Inform female patients of reproductive potential that use of CONZIP for an extended period of time during pregnancy can result in neonatal opioid withdrawal syndrome, which may be life-threatening if not recognized and treated [see Warnings and Precautions (5.5), Use in Specific Populations (8.1)].

Embryo-Fetal Toxicity

Inform female patients of reproductive potential that CONZIP can cause fetal harm and to inform their healthcare provider of a known or suspected pregnancy [see Use in Specific Populations (8.1)].

Lactation

Advise women that breastfeeding is not recommended during treatment with CONZIP [see Use in Specific Populations (8.2)].

Infertility

Inform patients that use of opioids for an extended period of time may cause reduced fertility. It is not known whether these effects on fertility are reversible [see Adverse Reactions (6.2), Use in Specific Populations (8.3)].

Manufactured by: | Galephar P.R., Inc. Juncos, Puerto Rico 00777
Distributed by: | Vertical Pharmaceuticals, LLC Alpharetta, GA 30005, USA

Medication Guide
CONZIP [KON-zip] (tramadol hydrochloride extended-release capsules), CIV

CONZIP is:

- A strong prescription pain medicine that contains an opioid (narcotic) that is used to manage severe and persistent pain that requires an extended treatment period with a daily opioid pain medicine when other pain medicines do not treat your pain well enough or you cannot tolerate them.
- A long-acting (extended-release) opioid pain medicine that can put you at risk for overdose and death. Even if you take your dose correctly as prescribed you are at risk for opioid addiction, abuse, and misuse that can lead to death.
- Not to be taken on an "as needed" basis.

Important information about CONZIP:

- Get emergency help right away or call 911 right away if you take too much CONZIP (overdose). When you first start taking CONZIP, when your dose is changed, or if you take too much (overdose), serious or life-threatening breathing problems that can lead to death may occur. Ask your healthcare provider about medicines like naloxone or nalmefene that can be used in an emergency to reverse an opioid overdose.
- Taking CONZIP with other opioid medicines, benzodiazepines, gabapentinoids (gabapentin or pregabalin), alcohol, or other central nervous system depressants (including street drugs) can cause severe drowsiness, decreased awareness, breathing problems, coma, and death.
- Never give anyone else your CONZIP. They could die from taking it. Selling or giving away CONZIP is against the law.
- Store CONZIP securely, out of sight and reach of children, and in a location not accessible by others, including visitors to the home.

Important Information Guiding Use in Pediatric Patients:

- Do not give CONZIP to a child younger than 12 years of age.
- Do not give CONZIP to a child younger than 18 years of age after surgery to remove the tonsils and/or adenoids.
- Avoid giving CONZIP to children between 12 to 18 years of age who have risk factors for breathing problems such as obstructive sleep apnea, obesity, or underlying lung problems.

Do not take CONZIP if you have:

- severe asthma, trouble breathing, or other lung problems.
- a bowel blockage or have narrowing of the stomach or intestines.

Before taking CONZIP, tell your healthcare provider if you have a history of:

- head injury, seizures
- problems urinating

- liver, kidney, thyroid problems
- pancreas or gallbladder problems

- abuse of street or prescription drugs, alcohol addiction, opioid overdose, or mental health problems.

Tell your healthcare provider if you are:

- noticing your pain getting worse. If your pain gets worse after you take CONZIP, do not take more of CONZIP without first talking to your healthcare provider. Talk to your healthcare provider if the pain that you have increases, if you feel more sensitive to pain, or if you have new pain after taking CONZIP.
- pregnant or planning to become pregnant. Use of CONZIP for an extended period of time during pregnancy can cause withdrawal symptoms in your newborn baby that could be life-threatening if not recognized and treated.
- breastfeeding. Not recommended during treatment with CONZIP; it may harm your baby.
- living in a household where there are small children or someone who has abused street or prescription drugs.
- taking prescription or over-the-counter medicines, vitamins, or herbal supplements. Taking CONZIP with certain other medicines can cause serious side effects that could lead to death.

When taking CONZIP:

- Do not change your dose. Take CONZIP exactly as prescribed by your healthcare provider. Use the lowest dose possible for the shortest time needed.
- Take your prescribed dose once a day at the same time every day. Do not take more than your prescribed dose. If you miss a dose, take your next dose at your usual time.
- Swallow CONZIP whole. Do not split, break, chew, crush, dissolve, snort, or inject CONZIP because this may cause you to overdose and die.
- Call your healthcare provider if the dose you are taking does not control your pain.
- Do not stop taking CONZIP without talking to your healthcare provider.
- Dispose of expired, unwanted, or unused CONZIP by taking your drug to an authorized DEA-registered collector or drug take-back program. If one is not available, you can dispose of CONZIP by mixing the product with dirt, cat litter, or coffee grounds; placing the mixture in a sealed plastic bag and throwing the bag in your trash. Visit www.fda.gov/drugdisposal for additional information on disposal of unused medicines.

While taking CONZIP DO NOT:

- Drive or operate heavy machinery, until you know how CONZIP affects you. CONZIP can make you sleepy, dizzy, or lightheaded.
- Drink alcohol or use prescription or over-the-counter medicines that contain alcohol. Using products containing alcohol during treatment with CONZIP may cause you to overdose and die.

The possible side effects of CONZIP:

- constipation, nausea, sleepiness, vomiting, tiredness, headache, dizziness, abdominal pain, seizure. Call your healthcare provider if you have any of these symptoms and they are severe.

Get emergency medical help or call 911 right away if you have:

- trouble breathing, shortness of breath, fast heartbeat, chest pain, swelling of your face, tongue, or throat, extreme drowsiness, light-headedness when changing positions, feeling faint, agitation, high body temperature, trouble walking, stiff muscles, or mental changes such as confusion.

These are not all the possible side effects of CONZIP. Call your healthcare provider for medical advice about side effects. You may report side effects to Vertical Pharmaceuticals, LLC at 1-800-541-4802 or FDA at 1-800-FDA-1088. For more information go to dailymed.nlm.nih.gov
Distributed by: Vertical Pharmaceuticals, LLC, Alpharetta, GA 30005, USA, call 1-800-541-4802.

This Medication Guide has been approved by the U.S. Food and Drug Administration.

Revised: December 2025

PRINCIPAL DISPLAY PANEL - 100 mg Capsule Bottle Label

NDC 68025-071-30

ConZip®
(tramadol hydrochloride)
extended-release capsules

CIV

100 mg per capsule

Once daily
Rx Only

VERTICAL
PHARMACEUTICALS, LLC

30 Capsules

PRINCIPAL DISPLAY PANEL - 200 mg Capsule Bottle Label

NDC 68025-072-30

ConZip®
(tramadol hydrochloride)
extended-release capsules

CIV

200 mg per capsule

Once daily
Rx Only

VERTICAL
PHARMACEUTICALS, LLC

30 Capsules

PRINCIPAL DISPLAY PANEL - 300 mg Capsule Bottle Label

NDC 68025-073-30

ConZip®
(tramadol hydrochloride)
extended-release capsules

CIV

300 mg per capsule

Once daily
Rx Only

VERTICAL
PHARMACEUTICALS, LLC

30 Capsules